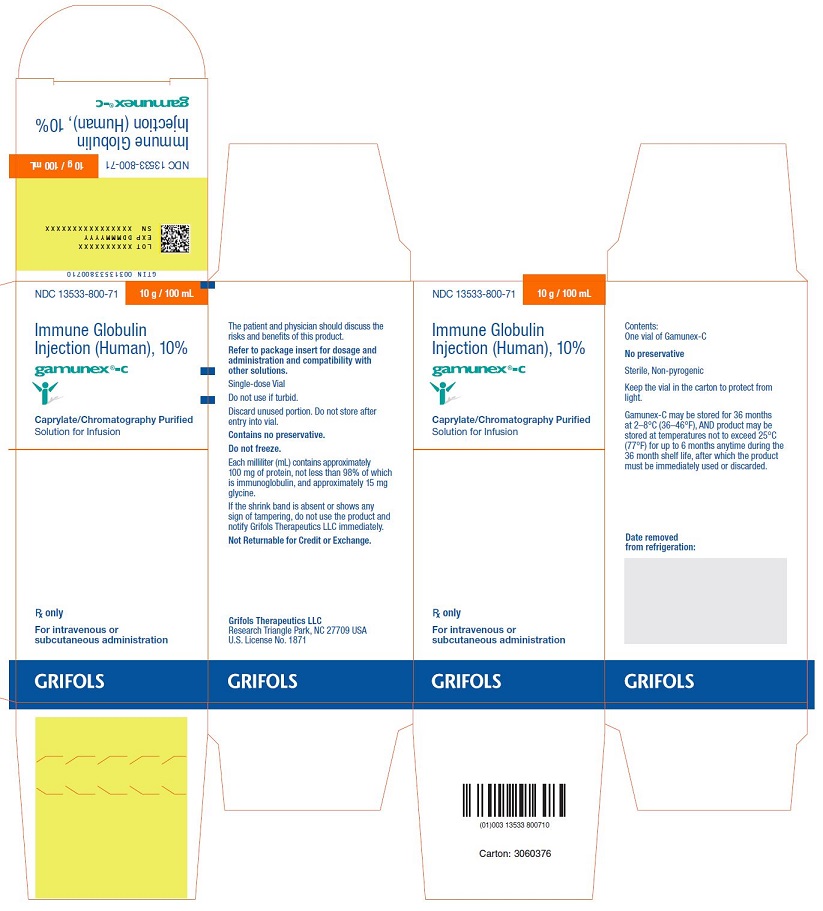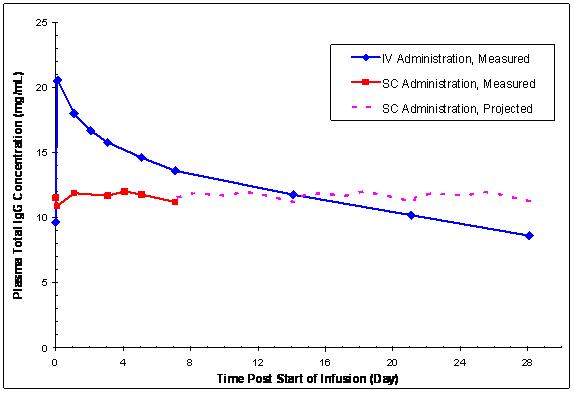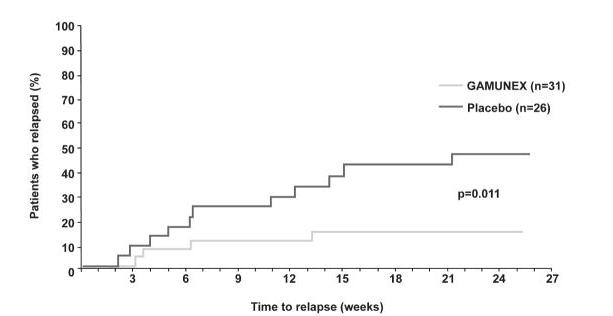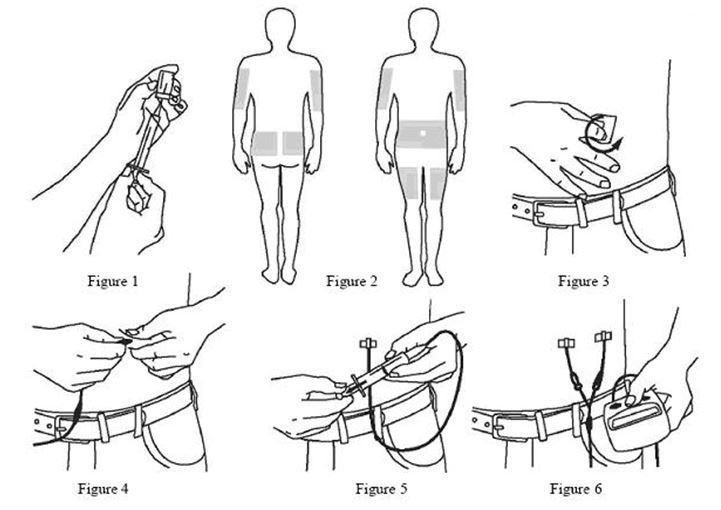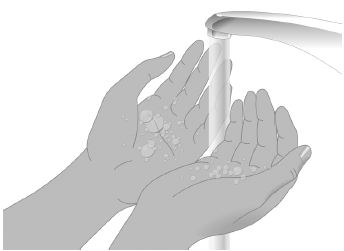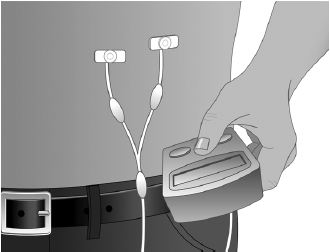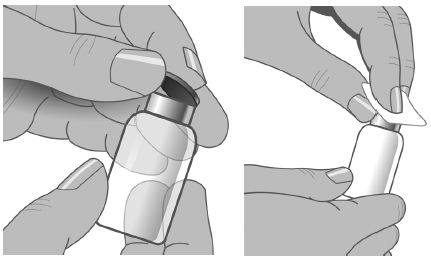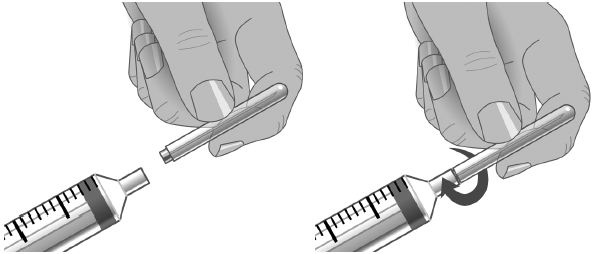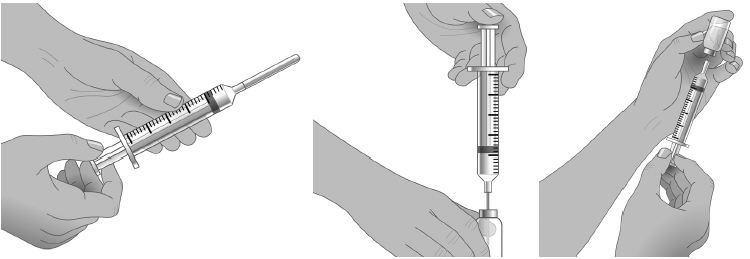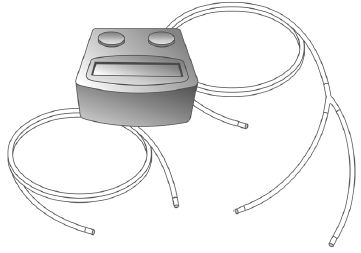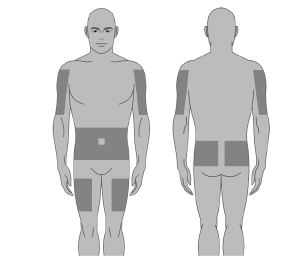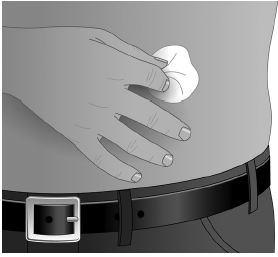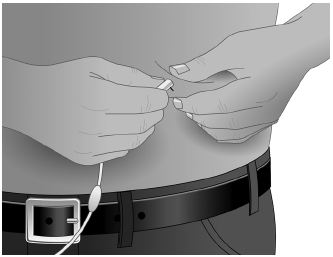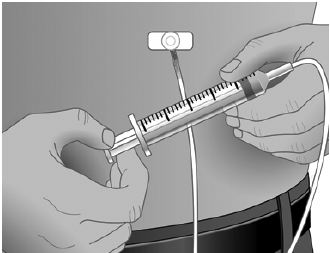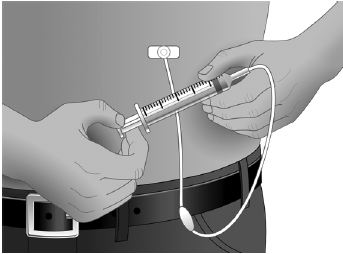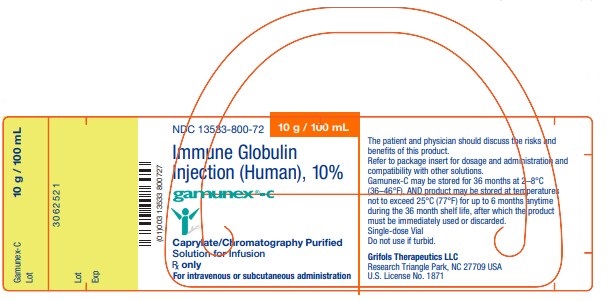 DRUG LABEL: Gamunex-C 
NDC: 13533-800 | Form: INJECTION
Manufacturer: GRIFOLS USA, LLC
Category: other | Type: PLASMA DERIVATIVE
Date: 20220429

ACTIVE INGREDIENTS: Human Immunoglobulin G 10 g/100 mL
INACTIVE INGREDIENTS: Glycine; Water

HIGHLIGHTS OF PRESCRIBING INFORMATION

These highlights do not include all the information needed to use GAMUNEX®-C safely and effectively. See full prescribing information for GAMUNEX-C.
GAMUNEX®-C, [Immune Globulin Injection (Human), 10% Caprylate/Chromatography Purified]
Initial U.S. Approval: 2003

WARNING: THROMBOSIS, RENAL DYSFUNCTION, and ACUTE RENAL FAILURE

See full prescribing information for complete boxed warning.

- Thrombosis may occur with immune globulin products, including GAMUNEX-C. Risk factors may include: advanced age, prolonged immobilization, hypercoagulable conditions, history of venous or arterial thrombosis, use of estrogens, indwelling vascular catheters, hyperviscosity, and cardiovascular risk factors.
- For patients at risk of thrombosis, administer GAMUNEX-C at the minimum dose and infusion rate practicable. Ensure adequate hydration in patients before administration. Monitor for signs and symptoms of thrombosis and assess blood viscosity in patients at risk for hyperviscosity.
- Renal dysfunction, acute renal failure, osmotic nephrosis, and death may occur with immune globulin intravenous (IGIV) products in predisposed patients.
- Renal dysfunction and acute renal failure occur more commonly in patients receiving IGIV products containing sucrose. GAMUNEX-C does not contain sucrose.
- For patients at risk of renal dysfunction or failure, administer GAMUNEX-C at the minimum concentration available and the minimum infusion rate practicable. (5.2)

1 INDICATIONS AND USAGE

GAMUNEX-C is an immune globulin injection (human), 10% liquid indicated for treatment of:

- Primary Humoral Immunodeficiency (PI) in patients 2 years of age and older (1.1)
- Idiopathic Thrombocytopenic Purpura (ITP) in adults and children (1.2)
- Chronic Inflammatory Demyelinating Polyneuropathy (CIDP) in adults (1.3)

2 DOSAGE AND ADMINISTRATION

Intravenous Administration Only: ITP and CIDP

Indication | Dose | Initial Infusion Rate | Maintenance Infusion Rate (if tolerated)
ITP (2.3) | 2 g/kg | 1 mg/kg/min | 8 mg/kg/min
CIDP (2.4) | loading dose 2 g/kg maintenance dose 1 g/kg | 2 mg/kg/min | 8 mg/kg/min Every 3 weeks

- Ensure that patients with pre-existing renal insufficiency are not volume depleted; discontinue GAMUNEX-C if renal function deteriorates. (5.2)
- For patients at risk of renal dysfunction or thrombosis, administer GAMUNEX-C at the minimum infusion rate practicable. (5.2, 5.4)

Intravenous or Subcutaneous Administration: PI (2.2)
DO NOT ADMINISTER SUBCUTANEOUSLY FOR ITP PATIENTS (5.10)

Route of Administration | Dose [See section 2.2.] | Initial Infusion Rate | Maintenance Infusion Rate (if tolerated)
Intravenous (IV) | 300 – 600 mg/kg | 1 mg/kg/min | 8 mg/kg/min Every 3 to 4 weeks
Subcutaneous (SC) | 1.37 x current IV dose in grams/IV dose interval in weeks | Adult: [Adults: use up to 8 infusion sites simultaneously; pediatric: use up to 6 infusion sites simultaneously; for all ages, ensure infusion sites are at least 2 inches (5 cm) apart. (2.5)] 20 mL/hr/site Pediatric: 10 mL/hr/site (< 25 kg) 15 mL/hr/site (≥ 25 kg) | Adult: 20 mL/hr/site Pediatric 10 mL/hr/site (< 25 kg) 20 mL/hr/site (≥ 25 kg) Weekly

3 DOSAGE FORMS AND STRENGTHS

GAMUNEX-C is a sterile solution for injection supplied in 1 g (10 mL), 2.5 g (25 mL), 5 g (50 mL), 10 g (100 mL), 20 g (200 mL), or 40 g (400 mL) single use vials. (3)

4 CONTRAINDICATIONS

- Anaphylactic or severe systemic reactions to human immunoglobulin (4.1)
- IgA deficient patients with antibodies against IgA and a history of hypersensitivity (4.2)

5 WARNINGS AND PRECAUTIONS

- IgA deficient patients with antibodies against IgA are at greater risk of developing severe hypersensitivity and anaphylactic reactions. Have epinephrine available immediately to treat any acute severe hypersensitivity reactions. (5.1)
- Hyperproteinemia, with resultant changes in serum viscosity and electrolyte imbalances may occur in patients receiving IGIV therapy. (5.3)
- Aseptic Meningitis Syndrome (AMS) may occur, especially with high doses or rapid infusion. (5.5)
- Hemolysis, either intravascular or due to enhanced RBC sequestration, can develop subsequent to GAMUNEX-C treatments. Risk factors include high doses and non-O blood group. Closely monitor patients for hemolysis and hemolytic anemia, especially in patients with pre-existing anemia and/or cardiovascular or pulmonary compromise. (5.6)
- Monitor patients for pulmonary adverse reactions (transfusion-related acute lung injury [TRALI]). (5.7)
- Volume overload. (5.8)
- GAMUNEX-C is made from human plasma and may carry a risk of transmitting infectious agents, e.g., viruses, the variant Creutzfeldt-Jakob disease (vCJD) agent and, theoretically, the Creutzfeldt-Jakob disease (CJD) agent. (5.9)
- GAMUNEX-C is not approved for subcutaneous use in ITP patients. Due to a potential risk of hematoma formation, do not administer GAMUNEX-C subcutaneously in patients with ITP. (5.10)
- Passive transfer of antibodies may confound serologic testing. (5.12)

6 ADVERSE REACTIONS

The most common adverse reactions observed in ≥ 5% patients were: (6.1)

PI: Intravenous: Cough increased, rhinitis, pharyngitis, headache, asthma, nausea, fever, diarrhea, and sinusitis.
Subcutaneous: Local infusion site reactions, fatigue, headache, upper respiratory tract infection, arthralgia, diarrhea, nausea, sinusitis, bronchitis, depression, allergic dermatitis, erythema, migraine, myalgia, viral infection, and pyrexia.

ITP: Headache, ecchymosis, vomiting, fever, nausea, rash, abdominal pain, back pain and dyspepsia.

CIDP: Headache, pyrexia, hypertension, chills, rash, nausea, arthralgia, and asthenia.

To report SUSPECTED ADVERSE REACTIONS, contact Grifols Therapeutics LLC at 1-800-520-2807 or FDA at 1-800-FDA-1088 or www.fda.gov/medwatch.

7 DRUG INTERACTIONS

- The passive transfer of antibodies may transiently interfere with the response to live virus vaccines, such as measles, mumps and rubella. (7)

8 USE IN SPECIFIC POPULATIONS

- Geriatric: In patients over 65 years of age do not exceed the recommended dose, and infuse GAMUNEX-C at the minimum infusion rate practicable. (8.5)

FULL PRESCRIBING INFORMATION

WARNING: THROMBOSIS, RENAL DYSFUNCTION, and ACUTE RENAL FAILURE

- Thrombosis may occur with immune globulin products, including GAMUNEX-C. Risk factors may include: advanced age, prolonged immobilization, hypercoagulable conditions, history of venous or arterial thrombosis, use of estrogens, indwelling central vascular catheters, hyperviscosity, and cardiovascular risk factors. Thrombosis may occur in the absence of known risk factors. [see Warnings and Precautions (5.4), Patient Counseling Information (17)]
- For patients at risk of thrombosis, administer GAMUNEX-C at the minimum dose and infusion rate practicable. Ensure adequate hydration in patients before administration. Monitor for signs and symptoms of thrombosis and assess blood viscosity in patients at risk for hyperviscosity. [see Dosage and Administration (2.5), Warnings and Precautions (5.4)]
- Renal dysfunction, acute renal failure, osmotic nephrosis, and death may occur with immune globulin intravenous (IGIV) products in predisposed patients. Patients predisposed to renal dysfunction include those with any degree of pre-existing renal insufficiency, diabetes mellitus, age greater than 65, volume depletion, sepsis, paraproteinemia, or patients receiving known nephrotoxic drugs.
- Renal dysfunction and acute renal failure occur more commonly in patients receiving IGIV products containing sucrose. GAMUNEX-C does not contain sucrose.
- For patients at risk of renal dysfunction or failure, administer GAMUNEX-C at the minimum concentration available and the minimum infusion rate practicable. [see Warnings and Precautions (5.2)]

1 INDICATIONS AND USAGE

GAMUNEX-C is an immune globulin injection (human) 10% liquid that is indicated for the treatment of:

1.1 Primary Humoral Immunodeficiency (PI)

GAMUNEX-C is indicated for treatment of primary humoral immunodeficiency in patients 2 years of age and older. This includes, but is not limited to, congenital agammaglobulinemia, common variable immunodeficiency, X-linked agammaglobulinemia, Wiskott-Aldrich syndrome, and severe combined immunodeficiencies.(1-4)

1.2 Idiopathic Thrombocytopenic Purpura (ITP)

GAMUNEX-C is indicated for the treatment of adults and children with Idiopathic Thrombocytopenic Purpura to raise platelet counts to prevent bleeding or to allow a patient with ITP to undergo surgery.(5,6)

1.3 Chronic Inflammatory Demyelinating Polyneuropathy (CIDP)

GAMUNEX-C is indicated for the treatment of CIDP in adults to improve neuromuscular disability and impairment and for maintenance therapy to prevent relapse.

2 DOSAGE AND ADMINISTRATION

2.1 Preparation and Handling

- Visually inspect GAMUNEX-C for particulate matter and discoloration prior to administration, whenever solution and container permit. Do not use if turbid.
- Do not freeze. Do not use solutions that have been frozen.
- Prior to use, allow the solution to reach ambient room temperature.
- If the packaging shows any signs of tampering, do not use the product and notify Grifols Therapeutics LLC immediately [1-800-520-2807].
- The GAMUNEX-C vial is for single use only. GAMUNEX-C contains no preservative. Use any vial that has been entered promptly. Discard partially used vials. Do not store after entry into vial.
- Infuse GAMUNEX-C using a separate line by itself, without mixing with other intravenous fluids or medications the subject might be receiving.
  The GAMUNEX-C infusion line can be flushed with 5% dextrose in water (D5/W) or 0.9% sodium chloride for injection.
- If dilution is required, GAMUNEX-C may be diluted with 5% dextrose in water (D5/W). Do not dilute with saline.
- Content of vials may be pooled under aseptic conditions into sterile infusion bags and infused within 8 hours after pooling.
- Avoid simultaneous administration of GAMUNEX-C and Heparin through a single lumen delivery device due to GAMUNEX-C, Heparin incompatibilities. Flush Heparin Lock (Hep-Lock) through which GAMUNEX-C was administered with 5% dextrose in water (D5/W) or 0.9% sodium chloride for injection, and do not flush with Heparin. See table below.

Additional Solutions | Dilution | Line Flush | Delivery Device Flush
5% Dextrose in water | Yes | Yes | Yes
0.9% Sodium Chloride | No | Yes | Yes
Heparin | No | No | No

- Do not mix with immune globulin intravenous (IGIV) products from other manufacturers.
- Do not use after expiration date.

2.2 PI

As there are significant differences in the half-life of IgG among patients with primary humoral immunodeficiencies, the ideal frequency and amount of immunoglobulin therapy may vary from patient to patient. The proper amount can be determined by monitoring clinical response.

Intravenous (IV)
The dose of GAMUNEX-C for patients with PI is 300 mg/kg to 600 mg/kg body weight (3 mL/kg to 6 mL/kg) administered every 3 to 4 weeks. The dosage may be adjusted over time to achieve the desired trough levels and clinical responses.

The recommended initial infusion rate is 1 mg/kg/min (0.01 mL/kg/min). If the infusion is well-tolerated, the rate may be gradually increased to a maximum of 8 mg/kg/min (0.08 mL/kg/min). For patients judged to be at risk for renal dysfunction or thrombosis, administer GAMUNEX-C at the minimum infusion rate practicable. [see Warnings and Precautions (5.2,5.4)]

If a patient routinely receives a dose of less than 400 mg/kg of GAMUNEX-C every 3 to 4 weeks (less than 4 mL/kg), and is at risk of measles exposure (i.e., traveling to a measles endemic area), administer a dose of at least 400 mg/kg (4 mL/kg) just prior to the expected measles exposure. If a patient has been exposed to measles, a dose of 400 mg/kg (4 mL/kg) should be administered as soon as possible after exposure.

Subcutaneous (SC)
The dose should be individualized based on the patient’s clinical response to GAMUNEX-C therapy and serum IgG trough levels. Begin treatment with GAMUNEX-C one week after the patient’s last IGIV infusion. See below under "Initial Weekly Dose". Prior to switching treatment from IGIV to GAMUNEX-C, obtain the patient’s serum IgG trough level to guide subsequent dose adjustments. See below under "Dose Adjustment".

Establish the initial weekly dose of GAMUNEX-C by converting the monthly IGIV dose into a weekly equivalent and increasing it using a dose adjustment factor. The goal is to achieve a systemic serum IgG exposure (Area Under the Concentration-Time Curve [AUC]) not inferior to that of the previous IGIV treatment. If the patient has not been previously treated with IV GAMUNEX-C, convert the monthly IGIV dose (in grams) by multiplying by 1.37, then dividing this dose into weekly doses based on the patient’s previous IGIV treatment interval. Monitor the patient’s clinical response, and adjust dose accordingly.

Initial Weekly Dose
To calculate the initial weekly dose of subcutaneous administration of GAMUNEX-C, multiply the previous IGIV dose in grams by the dose adjustment factor of 1.37; then divide this by the number of weeks between doses during the patient’s IGIV treatment (i.e., 3 or 4).

Initial SC dose (in grams) = 1.37 × previous IGIV dose (in grams)
Number of weeks between IGIV doses

To convert the GAMUNEX-C dose (in grams) to milliliters (mL), multiply the calculated Initial SC dose (in grams) by 10.

Dose Adjustment
Over time, the dose may need to be adjusted to achieve the desired clinical response and serum IgG trough level. To determine if a dose adjustment may be considered, measure the patient’s serum IgG trough level on IGIV and as early as 5 weeks after switching from IGIV to subcutaneous. The target serum IgG trough level on weekly SC treatment is projected to be the last IGIV trough level plus 340 mg/dL. To determine if further dose adjustments are necessary, monitor the patient’s IgG trough level every 2 to 3 months.

To adjust the dose based on trough levels, calculate the difference (in mg/dL) of the patient’s serum IgG trough level from the target IgG trough level (the last IGIV trough level + 340 mg/dL). Then find this difference in Table 1 and the corresponding amount (in mL) by which to increase or decrease the weekly dose based on the patient’s body weight. However, the patient’s clinical response should be the primary consideration in dose adjustment.

Table 1: Adjustment (±mL) of the Weekly Subcutaneous Dose Based on the Difference (±mg/dL) From the Target Serum IgG Trough Level
Difference From Target IgG Trough Level (mg/dL) | Body Weight (kg)
Difference From Target IgG Trough Level (mg/dL) | 10 | 15 | 20 | 30 | 40 | 50 | 60 | 70 | 80 | 90 | 100 | 110 | 120
Difference From Target IgG Trough Level (mg/dL) | Dose Adjustment (mL per Week) [Dose adjustment in mL is based on the slope of the serum IgG trough level response to subcutaneous administration of GAMUNEX-C dose increments (about 6.0 mg/dL per increment of 1 mg/kg per week).]
50 | 1 | 1 | 2 | 3 | 3 | 4 | 5 | 6 | 7 | 8 | 8 | 9 | 10
100 | 2 | 3 | 3 | 5 | 7 | 8 | 10 | 12 | 13 | 15 | 17 | 18 | 20
150 | 3 | 4 | 5 | 8 | 10 | 13 | 15 | 18 | 20 | 23 | 25 | 28 | 30
200 | 3 | 5 | 7 | 10 | 13 | 17 | 20 | 23 | 27 | 30 | 33 | 37 | 40
250 | 4 | 6 | 8 | 13 | 17 | 21 | 25 | 29 | 33 | 38 | 42 | 46 | 50
300 | 5 | 8 | 10 | 15 | 20 | 25 | 30 | 35 | 40 | 45 | 50 | 55 | 60
350 | 6 | 9 | 12 | 18 | 23 | 29 | 35 | 41 | 47 | 53 | 58 | 64 | 70
400 | 7 | 10 | 13 | 20 | 27 | 33 | 40 | 47 | 53 | 60 | 67 | 73 | 80
450 | 8 | 11 | 15 | 23 | 30 | 38 | 45 | 53 | 60 | 68 | 75 | 83 | 90
500 | 8 | 13 | 17 | 25 | 33 | 42 | 50 | 58 | 67 | 75 | 83 | 92 | 100

For example, if a patient with a body weight of 70 kg has an actual IgG trough level of 900 mg/dL and the target level is 1,000 mg/dL, this results in a difference of 100 mg/dL. Therefore, increase the weekly dose of subcutaneous dose by 12 mL.

Monitor the patient’s clinical response, and repeat the dose adjustment as needed.

Dosage requirements for patients switching to GAMUNEX-C from another Immune Globulin Subcutaneous (IGSC) product have not been studied. If a patient on GAMUNEX-C does not maintain an adequate clinical response or a serum IgG trough level equivalent to that of the previous IGSC treatment, adjust the dose accordingly. For such patients, Table 1 also provides guidance for dose adjustment to achieve a desired IGSC trough level.

2.3 ITP

DO NOT ADMINISTER SUBCUTANEOUSLY [see Warnings and Precautions (5.10)]

GAMUNEX-C may be administered at a total dose of 2 g/kg, divided in two doses of 1 g/kg (10 mL/kg) given on two consecutive days or into five doses of 0.4 g/kg (4 mL/kg) given on five consecutive days. If after administration of the first of two daily 1 g/kg (10 mL/kg) doses, an adequate increase in the platelet count is observed at 24 hours, the second dose of 1g/kg (10 mL/kg) body weight may be withheld.

The high dose regimen (1 g/kg × 1-2 days) is not recommended for individuals with expanded fluid volumes or where fluid volume may be a concern. [see Warnings and Precautions (5.8), Clinical Studies (14)]

The recommended initial infusion rate is 1 mg/kg/min (0.01 mL/kg/min). If the infusion is well-tolerated, the rate may be gradually increased to a maximum of 8 mg/kg/min (0.08 mL/kg/min). For patients judged to be at risk for renal dysfunction or thrombosis, administer GAMUNEX-C at the minimum infusion rate practicable. [see Warnings and Precautions (5.2,5.4)]

2.4 CIDP

GAMUNEX-C may be initially administered as a total loading dose of 2 g/kg (20 mL/kg) given in divided doses over two to four consecutive days. GAMUNEX-C may be administered as a maintenance infusion of 1 g/kg (10 mL/kg) administered over 1 day or divided into two doses of 0.5 g/kg (5 mL/kg) given on two consecutive days, every 3 weeks. Not all patients may require continued maintenance therapy beyond the initial 6 months of therapy in order to maintain their therapeutic response.

The recommended initial infusion rate is 2 mg/kg/min (0.02 mL/kg/min). If the infusion is well tolerated, the rate may be gradually increased to a maximum of 8 mg/kg/min (0.08 mL/kg/min). For patients judged to be at risk for renal dysfunction or thrombosis, administer GAMUNEX-C at the minimum infusion rate practicable. [see Warnings and Precautions (5.2,5.4)]

2.5 Administration

Administer intravenously for PI, ITP and CIDP.

GAMUNEX-C may also be administered subcutaneously for the treatment of PI.

- Administer GAMUNEX-C at room temperature.
- Inspect GAMUNEX-C visually for particulate matter and discoloration prior to administration, whenever the solution and container permit.
- Do not use if turbid and/or if discoloration is observed.

Intravenous

- Use only 18 gauge needles to penetrate the stopper for dispensing product from the 10 mL vial.
- Use 16 gauge needles or dispensing pins only with 25 mL vial sizes and larger.
- Insert needles or dispensing pins only once and be within the stopper area delineated by the raised ring.
- Penetrate the stopper perpendicular to the plane of the stopper within the ring.

GAMUNEX®-C vial size | Gauge of needle to penetrate stopper
10 mL | 18 gauge
25, 50, 100, 200, 400 mL | 16 gauge

- Use promptly any vial that has been opened.
- Discard partially used vials.
- If dilution is required, GAMUNEX-C may be diluted with 5% dextrose in water (D5/W). Do not dilute with saline. Infuse GAMUNEX-C using a separate line by itself, without mixing with other intravenous fluids or medications the subject might be receiving. The GAMUNEX-C infusion line can be flushed with 5% dextrose in water (D5/W) or 0.9% sodium chloride for injection.

Subcutaneous for PI Only

Instructions for Administration

- Prior to use, allow the solution to reach ambient room temperature.
- DO NOT SHAKE.
- Do not use if the solution is cloudy or has particulates.
- Check the product expiration date on the vial. Do not use beyond the expiration date.

1. Use aseptic technique when preparing and administering GAMUNEX-C for injection.
2. Remove the protective cap from the vial to expose the central portion of the stopper. If the packaging shows any sign of tampering, do not use the product and notify Grifols Therapeutics LLC immediately [1-800-520-2807].
3. Wipe the stopper with alcohol and allow to dry.
4. Using a sterile syringe and needle, prepare to withdraw GAMUNEX-C by first injecting air into the vial that is equivalent to the amount of GAMUNEX-C to be withdrawn. Then withdraw the desired volume of GAMUNEX-C. If multiple vials are required to achieve the desired dose, repeat this step. (Figure 1)
5. Follow the manufacturer’s instructions for filling the pump reservoir and preparing the pump, administration tubing and Y-site connection tubing, if needed. Be sure to prime the administration tubing to ensure that no air is left in the tubing or needle by filling the tubing/needle with GAMUNEX-C.
6. Select the number and location of injection sites. (Figure 2)
7. Cleanse the injection site(s) with antiseptic solution using a circular motion working from the center of the site and moving to the outside. Sites should be clean, dry, and at least two inches apart. (Figure 3)
8. Grasp the skin between two fingers and insert the needle into the subcutaneous tissue. (Figure 4)
9. After inserting each needle, make sure that a blood vessel has not been accidentally entered. Attach a sterile syringe to the end of the primed administration tubing, pull back on the plunger, and if you see blood, remove and discard the needle and administration tubing. (Figure 5)
10. Repeat priming and needle insertion steps using a new needle, administration tubing and a new infusion site. Secure the needle in place by applying sterile gauze or transparent dressing over the site.
11. If using multiple, simultaneous injection sites, use Y-site connection tubing and secure to the administration tubing.
12. Infuse GAMUNEX-C following the manufacturer’s instructions for the pump. (Figure 6)

Rate of Administration

Intravenous

Following initial infusion (see table below), the infusion rate may be gradually increased to a maximum of 0.08 mL/kg per minute (8 mg/kg per minute) as tolerated.

Indication | Initial Infusion Rate (first 30 minutes) | Maximum Infusion Rate (if tolerated)
PI | 1 mg/kg/min | 8 mg/kg/min
ITP | 1 mg/kg/min | 8 mg/kg/min
CIDP | 2 mg/kg/min | 8 mg/kg/min

Monitor patient vital signs throughout the infusion. Slow or stop infusion if adverse reactions occur. If symptoms subside promptly, the infusion may be resumed at a lower rate that is comfortable for the patient.

Certain severe adverse drug reactions may be related to the rate of infusion. Slowing or stopping the infusion usually allows the symptoms to disappear promptly.

Ensure that patients with pre-existing renal insufficiency are not volume depleted. For patients at risk of renal dysfunction or thrombosis, administer GAMUNEX-C at the minimum infusion rate practicable and discontinue GAMUNEX-C if renal function deteriorates.

Subcutaneous for PI Only

For PI, it is recommended that GAMUNEX-C is infused at a rate of 20 mL per hour per infusion site for adults, and up to 8 infusion sites may be used (most patients used 4 infusion sites). Children and adolescents weighing ≥ 25 kg should start out at a slower infusion rate of 15 mL/hour/infusion site and increase their infusion rate up to 20 mL/hour/infusion site. For children and adolescents weighing < 25 kg, a rate of 10 mL/hour/infusion site is recommended. In children up to 6 infusion sites simultaneously may be used. For patients of all ages ensure that the infusion sites are at least 2 inches (5 cm) apart.

3 DOSAGE FORMS AND STRENGTHS

GAMUNEX-C is a sterile solution for injection supplied in 1 g protein (10 mL), 2.5 g protein (25 mL), 5 g protein (50 mL), 10 g protein (100 mL), 20 g protein (200 mL), or 40 g protein (400 mL) single use vials.

4 CONTRAINDICATIONS

4.1 Hypersensitivity Reactions to Immune Globulins

GAMUNEX-C is contraindicated in patients who have had an anaphylactic or severe systemic reaction to the administration of human immune globulin.

4.2 IgA Sensitive Patients with History of Hypersensitivity Reaction

GAMUNEX-C is contraindicated in IgA deficient patients with antibodies against IgA and history of hypersensitivity.

5 WARNINGS AND PRECAUTIONS

5.1 Hypersensitivity

Severe hypersensitivity reactions may occur with IGIV products, including GAMUNEX-C. In case of hypersensitivity, discontinue GAMUNEX-C infusion immediately and institute appropriate treatment. Have medications such as epinephrine available for immediate treatment of acute hypersensitivity reaction.

GAMUNEX-C contains trace amounts of IgA (average 46 micrograms/mL). Patients with known antibodies to IgA may have a greater risk of developing potentially severe hypersensitivity and anaphylactic reactions. It is contraindicated in IgA deficient patients with antibodies against IgA and history of hypersensitivity reaction. [see Contraindications (4)]

5.2 Renal Failure

Acute renal dysfunction/failure, acute tubular necrosis, proximal tubular nephropathy, osmotic nephrosis and death may occur upon use of IGIV products, especially those containing sucrose.(7,8) GAMUNEX-C does not contain sucrose. Ensure that patients are not volume depleted prior to the initiation of the infusion of GAMUNEX-C. Periodic monitoring of renal function and urine output is particularly important in patients judged to have a potential increased risk for developing acute renal failure. Assess renal function, including measurement of blood urea nitrogen (BUN)/serum creatinine, prior to the initial infusion of GAMUNEX-C and again at appropriate intervals thereafter. If renal function deteriorates, consider discontinuation of GAMUNEX-C. [see Patient Counseling Information (17)] For patients judged to be at risk for developing renal dysfunction, including patients with any degree of pre-existing renal insufficiency, diabetes mellitus, age greater than 65, volume depletion, sepsis, paraproteinemia, or patients receiving known nephrotoxic drugs, administer GAMUNEX-C at the minimum infusion rate practicable [less than 8 mg/kg/min (0.08 mL/kg/min)]. [see Dosage and Administration (2.5)]

5.3 Hyperproteinemia, Increased Serum Viscosity, and Hyponatremia

Hyperproteinemia, increased serum viscosity and hyponatremia may occur in patients receiving IGIV treatment, including GAMUNEX-C. It is clinically critical to distinguish true hyponatremia from a pseudohyponatremia that is associated with concomitant decreased calculated serum osmolality or elevated osmolar gap, because treatment aimed at decreasing serum free water in patients with pseudohyponatremia may lead to volume depletion, a further increase in serum viscosity and a possible predisposition to thrombosis.(9)

5.4 Thrombosis

Thrombosis may occur following treatment with immune globulin products, including GAMUNEX-C.(10-12) Risk factors may include: advanced age, prolonged immobilization, hypercoagulable conditions, history of venous or arterial thrombosis, use of estrogens, indwelling central vascular catheters, hyperviscosity, and cardiovascular risk factors. Thrombosis may occur in the absence of known risk factors.

Consider baseline assessment of blood viscosity in patients at risk for hyperviscosity, including those with cryoglobulins, fasting chylomicronemia/markedly high triacylglycerols (triglycerides), or monoclonal gammopathies. For patients at risk of thrombosis, administer GAMUNEX-C at the minimum dose and infusion rate practicable. Ensure adequate hydration in patients before administration. Monitor for signs and symptoms of thrombosis and assess blood viscosity in patients at risk for hyperviscosity. [see Boxed Warning, Dosage and Administration (2.5), Patient Counseling Information (17)]

5.5 Aseptic Meningitis Syndrome (AMS)

AMS may occur infrequently with IGIV treatment, including GAMUNEX-C. Discontinuation of IGIV treatment has resulted in remission of AMS within several days without sequelae. The syndrome usually begins within several hours to two days following IGIV treatment. AMS is characterized by the following symptoms and signs: severe headache, nuchal rigidity, drowsiness, fever, photophobia, painful eye movements, nausea and vomiting. Cerebrospinal fluid (CSF) studies are frequently positive with pleocytosis up to several thousand cells per cu mm, predominantly from the granulocytic series, and with elevated protein levels up to several hundred mg/dL, but negative culture results. Conduct a thorough neurological examination on patients exhibiting such symptoms and signs including CSF studies, to rule out other causes of meningitis. AMS may occur more frequently in association with high doses (2 g/kg) and/or rapid infusion of IGIV.

5.6 Hemolysis

GAMUNEX-C may contain blood group antibodies which may act as hemolysins and induce in vivo coating of red blood cells (RBCs) with immunoglobulin, causing a positive direct antiglobulin reaction and hemolysis.(13-16) Delayed hemolytic anemia can develop subsequent to IGIV therapy due to enhanced RBC sequestration, and acute hemolysis consistent with intravascular hemolysis, has been reported. [see Adverse Reactions (6)]

The following risk factors may be related to the development of hemolysis: high doses (e.g., ≥ 2 grams/kg, single administration or divided over several days) and non-O blood group.(17) Underlying inflammatory state in an individual patient may increase the risk of hemolysis, but its role is uncertain.(18)

Closely monitor patients for clinical signs and symptoms of hemolysis [see Warnings and Precautions (5.11)], particularly patients with risk factors noted above and those with pre-existing anemia and/or cardiovascular or pulmonary compromise. Consider appropriate laboratory testing in higher risk patients, including measurement of hemoglobin or hematocrit prior to infusion and within approximately 36 hours and again 7 to 10 days post infusion. If clinical signs and symptoms of hemolysis or a significant drop in hemoglobin or hematocrit have been observed, perform additional confirmatory laboratory testing. If transfusion is indicated for patients who develop hemolysis with clinically compromising anemia after receiving IGIV, perform adequate cross-matching to avoid exacerbating on-going hemolysis.

5.7 Transfusion-related Acute Lung Injury (TRALI)

Noncardiogenic pulmonary edema may occur in patients following treatment with IGIV products, including GAMUNEX-C.(19) TRALI is characterized by severe respiratory distress, pulmonary edema, hypoxemia, normal left ventricular function, and fever. Symptoms typically occur within 1 to 6 hours after treatment.

Monitor patients for pulmonary adverse reactions. [see Patient Counseling Information (17)] If TRALI is suspected, perform appropriate tests for the presence of anti-neutrophil and anti-HLA antibodies in both the product and patient serum. TRALI may be managed using oxygen therapy with adequate ventilatory support.

5.8 Volume Overload

The high dose regimen (1 g/kg x 1-2 days) is not recommended for individuals with expanded fluid volumes or where fluid volume may be a concern.

5.9 Transmission of Infectious Agents

Because GAMUNEX-C is made from human blood, it may carry a risk of transmitting infectious agents, e.g., viruses, the variant Creutzfeldt-Jakob disease (vCJD) agent and, theoretically, the Creutzfeldt-Jakob disease (CJD) agent. No cases of transmission of viral diseases, vCJD or CJD have ever been identified for GAMUNEX-C. ALL infections suspected by a physician possibly to have been transmitted by this product should be reported by the physician or other healthcare provider to Grifols Therapeutics LLC [1-800-520-2807].

5.10 Hematoma Formation

Do not administer GAMUNEX-C subcutaneously in patients with ITP because of the risk of hematoma formation.

5.11 Monitoring: Laboratory Tests

- Periodic monitoring of renal function and urine output is particularly important in patients judged to be at increased risk of developing acute renal failure. Assess renal function, including measurement of BUN and serum creatinine, before the initial infusion of GAMUNEX-C and at appropriate intervals thereafter.
- Consider baseline assessment of blood viscosity in patients at risk for hyperviscosity, including those with cryoglobulins, fasting chylomicronemia/markedly high triacylglycerols (triglycerides), or monoclonal gammopathies, because of the potentially increased risk of thrombosis.
- If signs and/or symptoms of hemolysis are present after an infusion of GAMUNEX-C, perform appropriate laboratory testing for confirmation.
- If TRALI is suspected, perform appropriate tests for the presence of anti-neutrophil antibodies and anti-HLA antibodies in both the product and patient’s serum.

5.12 Interference with Laboratory Tests

After infusion of IgG, the transitory rise of the various passively transferred antibodies in the patient’s blood may yield positive serological testing results, with the potential for misleading interpretation. Passive transmission of antibodies to erythrocyte antigens (e.g., A, B, and D) may cause a positive direct or indirect antiglobulin (Coombs) test.

6 ADVERSE REACTIONS

PI: Intravenous: The most common adverse reactions observed at a rate ≥ 5% in subjects with intravenous treatment in the clinical trials were cough increased, rhinitis, pharyngitis, headache, asthma, nausea, fever, diarrhea, and sinusitis.

PI: Subcutaneous: The most common adverse reactions observed at a rate ≥ 5% of subjects with subcutaneous treatment in the clinical trials were local infusion site reactions, fatigue, headache, upper respiratory tract infection, arthralgia, diarrhea, nausea, sinusitis, bronchitis, depression, allergic dermatitis, erythema, migraine, myalgia, viral infection, and pyrexia.

ITP: The most common adverse reactions observed at a rate ≥ 5% in subjects in the clinical trials were headache, ecchymosis, vomiting, fever, nausea, rash, abdominal pain, back pain and dyspepsia.

CIDP: The most common adverse reactions observed at a rate ≥ 5% in subjects in the clinical trial were headache, pyrexia, hypertension, chills, rash, nausea, arthralgia, and asthenia.

6.1 Clinical Trials Experience

Because clinical studies are conducted under widely varying conditions, adverse reaction rates observed in the clinical trials of one drug cannot be directly compared to rates in other clinical trials of another drug and may not reflect the rates observed in clinical practice.

PI: Intravenous Administration

The most serious adverse event observed in clinical study subjects receiving GAMUNEX-C IV for PI was an exacerbation of autoimmune pure red cell aplasia in one subject.

In four different clinical trials to study PI, out of 157 subjects treated with GAMUNEX-C, 4 subjects discontinued due to the following adverse events: Coombs negative hypochromic anemia, autoimmune pure red cell aplasia, arthralgia/hyperhidrosis/fatigue/myalgia/nausea and migraine.

In a study of 87 subjects, 9 subjects in each treatment group were pretreated with non-steroidal medication prior to infusion, such as diphenhydramine and acetaminophen.

Table 2 lists the adverse reactions reported by at least 5% of subjects during the 9-month treatment.

Table 2: Adverse Reactions Occurring in ≥ 5% of Subjects
Adverse Reactions | GAMUNEX®-C | GAMIMUNE® N, 10%
Adverse Reactions | No. of subjects: 87 | No. of subjects: 85
Adverse Reactions | No. of subjects with adverse reaction (percentage of all subjects) | No. of subjects with adverse reaction (percentage of all subjects)
Cough increased | 27 (31.0%) | 25 (29.4%)
Rhinitis | 21 (24.1%) | 24 (28.2%)
Headache | 13 (14.9%) | 17 (20.0%)
Pharyngitis | 14 (16.1%) | 16 (18.8%)
Asthma | 13 (14.9%) | 10 (11.8%)
Fever | 6 (6.9%) | 10 (11.8%)
Nausea | 10 (11.5%) | 9 (10.6%)
Diarrhea | 6 (6.9%) | 9 (10.6%)
Sinusitis | 5 (5.7%) | 6 (7.1%)
* An adverse reaction is an adverse event that meets any of the following 3 criteria: (a) that began during or within 72 hours of the end of product infusion, (b) that was considered at least possibly related by either the investigator or the applicant, and/or (c) whose causality assessment by the investigator was missing or indeterminate.

Table 3 lists the frequency of adverse reactions (as defined for Table 2), which were reported by at least 5% of subjects.

Table 3: Adverse Reactions Frequency
Adverse Reactions | GAMUNEX®-C | GAMIMUNE® N, 10%
Adverse Reactions | No. of infusions: 825 | No. of infusions: 865
Adverse Reactions | Number (percentage of all infusions) | Number (percentage of all infusions)
Cough increased | 40 (4.8%) | 47 (5.4%)
Rhinitis | 34 (4.1%) | 44 (5.1%)
Headache | 17 (2.1%) | 24 (2.8%)
Pharyngitis | 20 (2.4%) | 24 (2.8%)
Fever | 8 (1.0%) | 20 (2.3%)
Asthma | 17 (2.1%) | 12 (1.4%)
Diarrhea | 10 (1.2%) | 10 (1.2%)
Nausea | 10 (1.2%) | 10 (1.2%)
Sinusitis | 6 (0.7%) | 7 (0.8%)

The mean number of adverse reactions per infusion that occurred during or within 72 hours of the end of product infusion was 0.33 for the GAMUNEX-C and 0.39 for the GAMIMUNE® N, 10% [Immune Globulin Intravenous (Human), 10%] treatment group.

In all three trials in primary humoral immunodeficiencies, the maximum infusion rate was 0.08 mL/kg/min (8 mg/kg/min). The infusion rate was reduced for 11 of 222 exposed subjects (7 GAMUNEX-C, 4 GAMIMUNE N, 10%) at 17 occasions. In most instances, mild to moderate hives/urticaria, itching, pain or reaction at infusion site, anxiety or headache was the main reason. There was one case of severe chills. There were no anaphylactic or anaphylactoid reactions to GAMUNEX-C or GAMIMUNE N, 10% in clinical trials.

In the IV efficacy and safety study, serum samples were drawn to monitor the virus safety at baseline and one week after the first infusion of IGIV (for parvovirus B19), eight weeks after first and fifth infusion of IGIV (for hepatitis C, hepatitis B, and HIV-1), 16 weeks after the first and fifth infusion of IGIV (for hepatitis C) and at any time of premature discontinuation of the study (for hepatitis C, hepatitis B, HIV-1, and parvovirus B19). Viral markers of hepatitis C, hepatitis B, HIV-1, and parvovirus B19 were monitored by nucleic acid testing (NAT, Polymerase Chain Reaction [PCR]) and serological testing. There were no treatment related emergent findings of virus transmission for either GAMUNEX-C or GAMIMUNE N, 10%.

PI: Subcutaneous Administration (PK and Safety Studies)

Adverse reactions were divided into 2 types: 1) Local infusion site reactions, and 2) Non-infusion site adverse reactions. Table 4 lists those adverse reactions (as defined for Table 2) occurring in ≥ 2% of infusions during the SC phase of two pharmacokinetic (PK) crossover and safety trials, one in adults and adolescents and the other in children and adolescents. [see Clinical Pharmacology (12.3)]

Table 4: Most Frequent Adverse Reactions (≥ 2% of infusions) by Infusion in the SC Phase
Adverse Reactions | Number (Rate [For each trial, rate is calculated by the total number of events divided by the number of infusions received (725 for the adult and adolescent trial and 121 for the children / adolescent trial).])
Adverse Reactions | Adult, Adolescent (Study 060001) | Child, Adolescent (Study T5004-401)
Non-infusion Site Adverse Reactions
Headache | 25 (0.03) | 1 (0.01)
Abdominal Pain | 1 (<0.01) | 2 (0.02)
Local Infusion Site Reactions [All local infusion site reactions were a priori considered drug-related.] , [At each level of summation (Preferred Term), local infusion site reactions are counted only once if they occur at the same infusion visit. Mild – usually transient in nature and generally not interfering with normal activities Moderate – sufficiently discomforting to interfere with normal activities Severe – prevents normal activities]
Mild | 389 (0.54) | 56 (0.46)
Moderate | 29 (0.04) | 4 (0.03)
Severe | 9 (0.01) | 1 (0.01)

Table 5 lists the adverse reactions occurring in ≥ 5% of subjects and the frequency of adverse reactions (as defined for Table 2) per infusion.

Table 5: Most Frequent Adverse Reactions (≥ 5% of subjects) by Subject and Infusion in the SC Phase
Adverse Reaction | Adult, Adolescent (Study 060001) |  | Child, Adolescent (Study T5004-401)
Adverse Reaction | No. of Subjects n=32 (%) | No. of Adverse Reactions (Rate [For each trial, rate is calculated by the total number of events divided by the number of infusions received (725 for the adult and adolescent trial and 121 for the children / adolescent trial).]) | No. of Subjects n=11 (%) | No. of Adverse Reactions (Rate)
Local Infusion Site Reaction [All local infusion site reactions were a priori considered drug-related] , [At each level of summation (Preferred Term), infusion site reactions are counted only once if they occur at the same infusion visit.] | 24 (75.0%) | 427 (0.59) | 11 (100%) | 61 (0.50)
Fatigue | 5 (15.6%) | 6 (0.01) | 0 | 0
Headache | 4 (12.5%) | 25 (0.03) | 1 (9.1%) | 1 (0.01)
Upper respiratory tract infection | 4 (12.5%) | 5 (0.01) | 1 (9.1%) | 1 (0.01)
Arthralgia | 3 (9.4%) | 6 (0.01) | 0 | 0
Diarrhea | 3 (9.4%) | 6 (0.01) | 0 | 0
Nausea | 3 (9.4%) | 4 (0.01) | 0 | 0
Sinusitis | 3 (9.4%) | 4 (0.01) | 0 | 0
Abdominal pain | 1 (3.1%) | 1 (<0.01) | 1 (9.1%) | 2 (0.02)
Abdominal pain upper | 0 | 0 | 1 (9.1%) | 1 (0.01)
Autoimmune thyroiditis | 0 | 0 | 1 (9.1%) | 1 (0.01)
Drug hypersensitivity | 0 | 0 | 1 (9.1%) | 1 (0.01)
Influenza | 0 | 0 | 1 (9.1%) | 1 (0.01)
Oropharyngeal pain | 0 | 0 | 1 (9.1%) | 1 (0.01)
Skin chapped | 0 | 0 | 1 (9.1%) | 1 (0.01)
Viral upper respiratory tract infection | 0 | 0 | 1 (9.1%) | 1 (0.01)
Wheezing | 1 (3.1%) | 1 (<0.01) | 1 (9.1%) | 1 (0.01)
Bronchitis | 2 (6.3%) | 2 (<0.01) | 0 | 0
Depression | 2 (6.3%) | 2 (<0.01) | 0 | 0
Dermatitis allergic | 2 (6.3%) | 2 (<0.01) | 0 | 0
Erythema | 2 (6.3%) | 2 (<0.01) | 0 | 0
Migraine | 2 (6.3%) | 2 (<0.01) | 0 | 0
Myalgia | 2 (6.3%) | 2 (<0.01) | 0 | 0
Pyrexia | 2 (6.3%) | 2 (<0.01) | 0 | 0
Viral infection | 2 (6.3%) | 2 (<0.01) | 0 | 0

There were no serious bacterial infections in the SC phase of the PK and safety trials.

Local Infusion Site Reactions

Local infusion site reactions with SC GAMUNEX-C consisted of erythema, pain and swelling. One child discontinued due to infusion site pain. The majority of local infusion site reactions resolved within 3 days. The number of subjects experiencing an infusion site reaction and the number of infusion site reactions decreased over time as subjects received continued weekly SC infusions. At the beginning of the SC phase (week 1) in the adult and adolescent trial, a rate of approximately 1 infusion site reaction per infusion was reported, whereas at the end of the study (week 24) this rate was reduced to 0.5 infusion site reactions per infusion, a reduction of 50%. In the children and adolescent trial, the rate of local infusion site reactions decreased from week 1 for all age groups by the end of the study.

ITP

In two different clinical trials to study ITP, out of 76 subjects treated with GAMUNEX-C, 2 subjects discontinued due to the following adverse reactions: Hives and Headache/Fever/Vomiting.

One subject, a 10-year-old boy, died suddenly from myocarditis 50 days after his second infusion of GAMUNEX-C. The death was judged to be unrelated to GAMUNEX-C.

No pre-medication with corticosteroids was permitted by the protocol. Twelve ITP subjects treated in each treatment group were pretreated with medication prior to infusion. Generally, diphenhydramine and/or acetaminophen were used. More than 90% of the observed drug related adverse events were of mild to moderate severity and of transient nature.

The infusion rate was reduced for 4 of the 97 exposed subjects (1 GAMUNEX-C, 3 GAMIMUNE N, 10%) on 4 occasions. Mild to moderate headache, nausea, and fever were the reported reasons.

Table 6 lists the adverse reactions (as defined for Table 2) reported by at least 5% of subjects during the 3-month efficacy and safety study.

Table 6: Adverse Reactions Occurring in ≥ 5% of Subjects
Adverse Reaction | GAMUNEX®-C No. of subjects: 48 Number (percentage of all subjects) | GAMIMUNE® N, 10% No. of subjects: 49 Number (percentage of all subjects)
Headache | 25 (52.1%) | 26 (53.1%)
Vomiting | 6 (12.5%) | 8 (16.3%)
Ecchymosis | 7 (14.6%) | 2 (4.1%)
Fever | 6 (12.5%) | 6 (12.2%)
Nausea | 6 (12.5%) | 5 (10.2%)
Rash | 4 (8.3%) | 0
Abdominal pain | 3 (6.3%) | 3 (6.1%)
Back pain | 3 (6.3%) | 2 (4.1%)
Dyspepsia | 3 (6.3%) | 0
Asthenia | 2 (4.2%) | 3 (6.1%)
Dizziness | 2 (4.2%) | 3 (6.1%)

Serum samples were drawn to monitor the virus safety of the ITP subjects at baseline, nine days after the first infusion (for parvovirus B19), and 3 months after the first infusion of IGIV and at any time of premature discontinuation of the study. Viral markers of hepatitis C, hepatitis B, HIV-1, and parvovirus B19 were monitored by nucleic acid testing (NAT, PCR), and serological testing. There were no treatment related emergent findings of virus transmission for either GAMUNEX-C or GAMIMUNE N, 10%.

CIDP

In the CIDP efficacy and safety study, 113 subjects were exposed to GAMUNEX-C and 95 were exposed to Placebo. [see Clinical Studies (14)] As a result of the study design, the drug exposure with GAMUNEX-C was almost twice that of Placebo, with 1096 GAMUNEX-C infusions versus 575 Placebo infusions. Therefore, adverse reactions are reported per infusion (represented as frequency) to correct for differences in drug exposure between the 2 groups. The majority of loading-doses were administered over 2 days. The majority of maintenance-doses were administered over 1 day. Infusions were administered in the mean over 2.7 hours.

Table 7 shows the numbers of subjects per treatment group in the CIDP clinical trial, and the reason for discontinuation due to adverse events.

Table 7: Reasons for Discontinuation Due to Adverse Events
Number of Subjects |  | Number of Subjects Discontinued due to Adverse Events | Adverse Event
GAMUNEX®-C | 113 | 3 (2.7%) | Urticaria, Dyspnea, Bronchopneumonia
Placebo | 95 | 2 (2.1%) | Cerebrovascular Accident, Deep Vein Thrombosis

The most common adverse reactions with GAMUNEX-C were headache and pyrexia. Table 8 lists adverse reactions (as defined for Table 2) reported by at least 5% of subjects in any treatment group.

Table 8: Adverse Reactions Occurring in ≥ 5% of Subjects
 | GAMUNEX®-C No. of subjects: 113 |  |  | Placebo No. of subjects: 95
MedDRA Preferred Term [Reported in ≥ 5% of subjects in any treatment group.] | No. of Subjects (%) | No. of Adverse Reactions | Incidence density [Calculated by the total number of adverse reactions divided by the number of infusions received (1096 for GAMUNEX-C and 575 for Placebo).] | No. of Subjects (%) | No. of Adverse Reactions | Incidence density
Headache | 35 (31.0%) | 50 | 0.046 | 7 (7.4%) | 9 | 0.016
Pyrexia | 15 (13.3%) | 27 | 0.025 | 0 | 0
Hypertension | 10 (8.8%) | 19 | 0.017 | 3 (3.2%) | 3 | 0.005
Chills | 9 (8.0%) | 10 | 0.009 | 0 | 0
Nausea | 7 (6.2%) | 9 | 0.008 | 3 (3.2%) | 3 | 0.005
Rash | 7 (6.2%) | 10 | 0.009 | 1 (1.1%) | 1 | 0.002
Arthralgia | 6 (5.3%) | 7 | 0.006 | 0 | 0
Asthenia | 6 (5.3%) | 6 | 0.005 | 1 (1.1%) | 2 | 0.003

The most serious adverse reaction observed in clinical study subjects receiving GAMUNEX-C for CIDP was pulmonary embolism (PE) in one subject with a history of PE.

Laboratory Abnormalities

During the course of the clinical program, ALT and AST elevations were identified in some subjects.

- For ALT, in the IV PI study treatment emergent elevations above the upper limit of normal were transient and observed among 14/80 (18%) of subjects in the GAMUNEX-C group versus 5/88 (6%) of subjects in the GAMIMUNE N, 10% group (p = 0.026).
- In the SC PI study treatment emergent laboratory abnormalities during the SC phase occurred in several subjects. Four subjects (4/32, 13%) had elevated Alkaline Phosphatase. One subject (1/32, 3%) had an elevated ALT and three subjects (3/32, 9%) had an elevated AST. No elevations were > 1.6 times the upper limit of normal.
- In the ITP study which employed a higher dose per infusion, but a maximum of only two infusions, the reverse finding for elevation of ALT was observed among 3/44 (7%) of subjects in the GAMUNEX-C group versus 8/43 (19%) of subjects in the GAMIMUNE N, 10% group (p = 0.118).
- In the CIDP study, 15/113 (13%) of subjects in the GAMUNEX-C group and 7/95 (7%) in the Placebo group (p=0.168) had a treatment emergent transient elevation of ALT.

Elevations of ALT and AST were generally mild (< 3 times upper limit of normal), transient, and were not associated with obvious symptoms of liver dysfunction.

GAMUNEX-C may contain low levels of anti-Blood Group A and B antibodies primarily of the IgG4 class. Direct antiglobulin tests (DAT or direct Coombs tests), which are carried out in some centers as a safety check prior to red blood cell transfusions, may become positive temporarily. There were 2 cases of hemolytic anemia across these clinical trials. One hemolytic event not associated with positive DAT findings was observed in the IV PI study in a woman with common variable immune deficiency and B12 deficiency (pernicious anemia) at a dose of (450 mg/kg). The other hemolytic event occurred in the CIDP study in a subject with positive DAT at a dose of 1g/kg.

6.2 Postmarketing Experience

Because adverse reactions are voluntarily reported post-approval from a population of uncertain size, it is not always possible to reliably estimate their frequencies or establish a causal relationship to product exposure.

The following adverse reactions have been identified during post-approval use of IGIV products, (8,20) including GAMUNEX-C:

- Infusion Reactions: Hypersensitivity (e.g., anaphylaxis), tachycardia, malaise, flushing, or other skin reactions, chest discomfort, rigors, and changes in blood pressure
- Renal: Acute renal dysfunction/failure, osmotic nephropathy
- Respiratory: Apnea, Acute Respiratory Distress Syndrome (ARDS), TRALI, cyanosis, hypoxemia, pulmonary edema, bronchospasm
- Cardiovascular: Cardiac arrest, thromboembolism, vascular collapse, hypotension
- Neurological: Coma, loss of consciousness, seizures/convulsions, tremor, aseptic meningitis
- Integumentary: Stevens-Johnson syndrome, epidermolysis, erythema multiforme, dermatitis (e.g., bullous dermatitis)
- Hematologic: Pancytopenia, leukopenia, hemolysis, hemolytic anemia, positive direct antiglobulin (Coombs test)
- General/Body as a Whole: Rigors
- Gastrointestinal: Hepatic dysfunction

7 DRUG INTERACTIONS

GAMUNEX-C may be diluted with 5% dextrose in water (D5/W). Do not dilute with saline. Admixtures of GAMUNEX-C with other drugs and intravenous solutions have not been evaluated. It is recommended that GAMUNEX-C be administered separately from other drugs or medications which the patient may be receiving. The product should not be mixed with IGIVs from other manufacturers.

The infusion line may be flushed before and after administration of GAMUNEX-C with 5% dextrose in water (D5/W) or 0.9% sodium chloride for injection.

Avoid simultaneous administration of GAMUNEX-C and Heparin through a single lumen delivery device due to GAMUNEX-C, Heparin incompatibilities. Flush Heparin Lock (Hep-Lock) through which GAMUNEX-C was administered with 5% dextrose in water (D5/W) or 0.9% sodium chloride for injection, and do not flush with Heparin.

Various passively transferred antibodies in immunoglobulin preparations can confound the results of serological testing.

Passive transfer of antibodies may transiently interfere with the immune response to live virus vaccines such as measles, mumps, rubella and varicella. Inform the immunizing physician of recent therapy with GAMUNEX-C so that appropriate measures may be taken. [see Patient Counseling Information (17)]

8 USE IN SPECIFIC POPULATIONS

8.1 Pregnancy

Risk Summary

There are no data with GAMUNEX-C use in pregnant women to inform a drug-associated risk. Animal reproduction studies have not been conducted with GAMUNEX-C. It is not known whether GAMUNEX-C can cause fetal harm when administered to a pregnant woman or can affect reproduction capacity. GAMUNEX-C should be given to a pregnant woman only if clearly needed. In the U.S. general population, the estimated background risk of major birth defect and miscarriage in clinically recognized pregnancies is 2-4% and 15-20%, respectively.

8.2 Lactation

Risk Summary

There is no information regarding the presence of GAMUNEX-C in human milk, the effect on the breastfed infant, and the effects on milk production. The developmental and health benefits of breastfeeding should be considered along with the mother’s clinical need for GAMUNEX-C and any potential adverse effects on the breastfed infant from GAMUNEX-C or from the underlying maternal condition.

8.4 Pediatric Use

PI: Intravenous

GAMUNEX-C was evaluated in 18 pediatric subjects (age range 0-16 years). Twenty-one percent of PI subjects exposed to GAMUNEX-C were children. Pharmacokinetics, safety and efficacy were similar to those in adults with the exception that vomiting was more frequently reported in pediatrics (3 of 18 subjects). No pediatric-specific dose requirements were necessary to achieve serum IgG levels.

PI: Subcutaneous

SC GAMUNEX-C was evaluated in three pediatric subjects (age range 13-15 years) with PI along with adults, and separately in a second trial in 11 children and adolescents (age range 2-16 years). Pharmacokinetics and safety were similar to those in adults. No pediatric-specific dose requirements were necessary to achieve circulating IgG levels. Efficacy and safety in pediatric patients under 2 years of age using the SC route of administration have not been established.

ITP

For treatment of ITP, GAMUNEX-C must be administered by the intravenous route.

GAMUNEX-C was evaluated in 12 pediatric subjects with acute ITP. Twenty-five percent of the acute ITP subjects exposed to GAMUNEX-C were children. Pharmacokinetics, safety and efficacy were similar to those in adults with the exception that fever was more frequently reported in pediatrics (6 of 12 subjects). No pediatric-specific dose requirements were necessary to achieve serum IgG levels. One subject, a 10-year-old boy, died suddenly from myocarditis 50 days after his second infusion of GAMUNEX-C. The death was judged to be unrelated to GAMUNEX-C.

CIDP

The safety and effectiveness of GAMUNEX-C have not been established in pediatric subjects with CIDP.

8.5 Geriatric Use

Use caution when administering GAMUNEX-C to patients age 65 and over who are at increased risk for thrombosis or renal insufficiency. [see Boxed Warning, Warnings and Precautions (5.2, 5.4)] Do not exceed recommended doses, and administer GAMUNEX-C at the minimum infusion rate practicable. Clinical studies of GAMUNEX-C did not include sufficient numbers of subjects aged 65 and over to determine whether they respond differently from younger subjects.

10 OVERDOSAGE

With intravenous administration, overdose of GAMUNEX-C may lead to fluid overload and hyperviscosity. Patients at risk of complications of fluid overload and hyperviscosity include elderly patients and those with cardiac renal impairment.

11 DESCRIPTION

GAMUNEX-C is a ready-to-use sterile, non-pyrogenic solution of human immune globulin protein for intravenous and subcutaneous (PI indication only) administration. GAMUNEX-C is clear to opalescent, and colorless to pale yellow. GAMUNEX-C consists of 9%–11% protein in 0.16–0.24 M glycine. Not less than 98% of the protein has the electrophoretic mobility of gamma globulin. The main component of GAMUNEX-C is IgG (≥ 98%) with a sub-class distribution of IgG1, IgG2, IgG3 and IgG4 of approximately 62.8%, 29.7%, 4.8% and 2.7% respectively. The distribution of IgG subclasses is similar to that found in normal serum.

GAMUNEX-C contains trace levels of fragments, IgA (average 0.046 mg/mL), and IgM. GAMUNEX-C doses of 1 g/kg correspond to a glycine dose of 0.15 g/kg. While toxic effects of glycine administration have been reported, the doses and rates of administration were 3–4 fold greater than those for GAMUNEX-C. In another study it was demonstrated that intravenous bolus doses of 0.44 g/kg glycine were not associated with serious adverse effects.(21) Caprylate is a saturated medium-chain (C8) fatty acid of plant origin. Medium chain fatty acids are considered to be essentially non-toxic. Human subjects receiving medium chain fatty acids parenterally have tolerated doses of 3.0 to 9.0 g/kg/day for periods of several months without adverse effects.(22) Residual caprylate concentrations in the final container are no more than 0.216 g/L (1.3 mmol/L). The measured buffer capacity is 35 mEq/L (0.35 mEq/g protein) and the osmolality is 258 mOsmol/kg solvent, which is close to physiological osmolality (285-295 mOsmol/kg). A dose of 1 g/kg body weight therefore represents an acid load of 0.35 mEq/kg body weight. The total buffering capacity of whole blood in a normal individual is 45–50 mEq/L of blood, or 3.6 mEq/kg body weight. Thus, the acid load delivered with a dose of 1 g/kg of GAMUNEX-C would be neutralized by the buffering capacity of whole blood alone, even if the dose was infused instantaneously. The pH of GAMUNEX-C is 4.0–4.5. GAMUNEX-C contains no preservative. GAMUNEX-C is not made with natural rubber latex.

GAMUNEX-C is made from large pools of human plasma by a combination of cold ethanol fractionation, caprylate precipitation and filtration, and anion-exchange chromatography. Isotonicity is achieved by the addition of glycine. GAMUNEX-C is incubated in the final container (at the low pH of 4.0–4.3). The product is intended for intravenous administration and may be administered subcutaneously in treatment of PI.

The capacity of the manufacturing process to remove and/or inactivate enveloped and non-enveloped viruses has been validated by laboratory spiking studies on a scaled down process model, using the following enveloped and non-enveloped viruses: human immunodeficiency virus, type I (HIV-1) as the relevant virus for HIV-1 and HIV–2; bovine viral diarrhea virus (BVDV) as a model for hepatitis C virus; pseudorabies virus (PRV) as a model for large enveloped DNA viruses (e.g., herpes viruses); Reovirus type 3 (Reo) as a model for non-enveloped viruses and for its resistance to physical and chemical inactivation; hepatitis A virus (HAV) as relevant non-enveloped virus, and porcine parvovirus (PPV) as a model for human parvovirus B19.(23)

Overall virus reduction was calculated only from steps that were mechanistically independent from each other and truly additive. In addition, each step was verified to provide robust virus reduction across the production range for key operating parameters.

Table 9: Log10 Virus Reduction
Process Step | Log10 Virus Reduction
Process Step | Enveloped Viruses |  |  | Non-enveloped Viruses
Process Step | HIV | PRV | BVDV | Reo | HAV | PPV
Caprylate Precipitation/Depth Filtration | C/I [C/I - Interference by caprylate precluded determination of virus reduction for this step. Although removal of viruses is likely to occur at the caprylate precipitation/depth filtration step, BVDV is the only enveloped virus for which reduction is claimed. The presence of caprylate prevents detection of other, less resistant enveloped viruses and therefore their removal cannot be assessed.] | C/I | 2.7 | ≥ 3.5 | ≥ 3.6 | 4.0
Caprylate Incubation | ≥ 4.5 | ≥ 4.6 | ≥ 4.5 | NA [NA - Not Applicable: This step has no effect on non-enveloped viruses.] | NA | NA
Depth Filtration [Some mechanistic overlap occurs between depth filtration and other steps. Therefore, Grifols Therapeutics LLC has chosen to exclude this step from the global virus reduction calculations.] | CAP [CAP - The presence of caprylate in the process at this step prevents detection of enveloped viruses, and their removal cannot be assessed.] | CAP | CAP | ≥ 4.3 | ≥ 2.0 | 3.3
Column Chromatography | ≥ 3.0 | ≥ 3.3 | 4.0 | ≥ 4.0 | ≥ 1.4 | 4.2
Nanofiltration | ≥ 3.7 | M/I [M/I - Interference by the process intermediate matrix precluded determination of virus removal capacity for this step.] | ≥ 4.1 | ≥ 1.8 | M/I | < 1.0
Low pH Incubation | ≥ 6.5 | ≥ 4.3 | ≥ 5.1 | NA | NA | NA
Global Reduction [Sum of reduction factors greater than or equal to 1 log10.] | ≥ 17.7 | ≥ 12.2 | ≥ 20.4 | ≥ 9.3 | ≥ 5.0 | 8.2

Additionally, the manufacturing process was investigated for its capacity to decrease the infectivity of an experimental agent of transmissible spongiform encephalopathy (TSE), considered as a model for the vCJD and CJD agents.(23)

Several of the individual production steps in the GAMUNEX-C manufacturing process have been shown to decrease TSE infectivity of that experimental model agent. TSE reduction steps include two depth filtrations (in sequence, a total of ≥ 6.6 log10). These studies provide reasonable assurance that low levels of CJD/vCJD agent infectivity, if present in the starting material, would be removed.

12 CLINICAL PHARMACOLOGY

12.1 Mechanism of Action

PI

GAMUNEX-C supplies a broad spectrum of opsonic and neutralizing IgG antibodies against bacterial, viral, parasitic, and mycoplasmal agents, and their toxins. The mechanism of action in PI has not been fully elucidated.

ITP

The mechanism of action of high doses of immunoglobulins in the treatment of ITP has not been fully elucidated.

CIDP

The precise mechanism of action in CIDP has not been fully elucidated.

12.3 Pharmacokinetics

Two pharmacokinetic crossover trials were carried out with GAMUNEX-C in 44 subjects with Primary Humoral Immunodeficiency to assess intravenous vs subcutaneous administration. In the first study, a single sequence, open-label, crossover trial in adults and adolescents, the pharmacokinetics, safety, and tolerability of SC administered GAMUNEX-C in subjects with PI were evaluated.(24) A total of 32 and 26 subjects received GAMUNEX-C as IV or SC for PK study, respectively, of whom 3 were adolescents. Subjects received GAMUNEX-C 200-600 mg/kg IV every 3-4 weeks for at least 3 months, at which time they entered the IV phase of the study. Subjects were crossed over to weekly SC infusions. The weekly SC dose was determined by multiplying the total IV dose by 1.37 and dividing the resultant new total dose by 3 or 4 depending on the previous IV interval.

In the second study, a single sequence, open-label, crossover trial, the pharmacokinetics, safety, and tolerability of SC administered GAMUNEX-C were evaluated in children and adolescents. The design of the study was essentially the same as above. A total of 11 subjects received GAMUNEX-C as IV and 10 received GAMUNEX-C as SC for PK analysis. Age groups were as follows: age 2 to 5 years, [N = 1 both phases]; 6 to 11 years, [N = 5 completing IV phase, N = 4 evaluated in SC phase]; 12-16 years: [N = 5 both phases].

Intravenous Administration

The pharmacokinetic parameters of GAMUNEX-C, measured as total IgG for intravenous administration are shown in Table 10.

Table 10: PK Parameters Following IV Administration of GAMUNEX®-C by Age
Age Group | Statistics | t1/2 (hr) | AUC(0-t) (hr*mg/mL) | AUC(0-tau) (hr*mg/mL) | CL(0-t) (mL/hr/kg) | Vss (mL/kg)
2 – 5 years N = 1 | Mean | 1038.50 | 7479.0 | 7499.0 | 0.05430 | 82.040
2 – 5 years N = 1 | SD [SD - standard deviation; NA - not applicable. Source: studies 060001, T5004-401] | NA | NA | NA | NA | NA
6 – 11 years N = 5 | Mean | 758.52 | 5953.6 | 6052.6 | 0.09128 | 94.784
6 – 11 years N = 5 | SD | 137.989 | 1573.84 | 1333.59 | 0.027465 | 17.6773
12 – 16 years N = 8 | Mean | 717.90 | 8131.9 | 8009.5 | 0.07029 | 73.303
12 – 16 years N = 8 | SD | 170.141 | 1173.38 | 1358.76 | 0.015912 | 17.2204
≥ 17 years N = 29 | Mean | 720.62 | 7564.9 | 7524.8 | 0.06243 | 65.494
≥ 17 years N = 29 | SD | 130.864 | 1190.68 | 1183.05 | 0.015547 | 18.7172

PI: Subcutaneous Administration

The PK parameter (AUC of total IgG) following IV and SC administration is summarized in Table 11 for subcutaneous vs intravenous administration in the two pharmacokinetic trials. In the adult and adolescent trial, the lower bound of the 90% confidence interval for the geometric mean ratio of AUC (SC vs. IV) was 0.861, therefore, meeting the pre-specified non-inferiority margin between the two modes of administration. The PK analysis results in children and adolescents are consistent to those in the adult and adolescent trial, demonstrating the appropriateness of the conversion factor of 1.37 applied to calculating the SC dose from the IV dose of GAMUNEX-C in pediatric populations.

Table 11: Summary of AUC of Total IgG at Steady State Following IV or SC Administration of GAMUNEX®-C by Age
Route of Administration | IV (N = 43) |  |  | SC (N = 36) | AUC Ratio, SC/IV
Age Group (N) Statistics | AUC0-τ,IV (h*mg/mL) (0-21 days) | AUC0-τ,IV (h*mg/mL) (0-28 days) | Adj._AUC0-τ,IV [Adj._AUC0-τ,IV: Adjusted weekly IV AUC(0-7 days) is calculated as AUC(0-21 days)/3 or AUC(0-28 days)/4.] (h*mg/mL) (0-7 days) | AUC0-τ,SC (h*mg/mL) (0-7 days) | AUC Ratio, SC/IV
2-5 years (N) |  | 1 | 1 | 1 | 1
Mean | NC [NC - not calculated Source: Studies 060001, T5004-401] | 7498.7 | 1874.7 | 2023.0 | 1.080
%CV | NC | NC | NC | NC | -
Range | NC | NC | NC | NC | NC
6-11 years (N) | 5 |  | 5 | 4 | 4
Mean | 6052.7 | NC | 2017.6 | 2389.2 | 1.135
%CV | 22% | NC | 22% | 19% | -
Range | 4868 - 8308 | NC | 1623 - 2769 | 1971 - 3039 | 1.10 - 1.21
12-16 years (N) | 5 | 3 | 8 | 7 | 7
Mean | 7396.0 | 9032.0 | 2387.6 | 2361.9 | 0.982
%CV | 17% | 9% | 15% | 14% | -
Range | 5271 - 8754 | 8504 - 9950 | 1757 - 2918 | 1876 - 2672 | 0.86 - 1.07
≥ 17 years (N) | 10 | 19 | 29 | 24 | 24
Mean | 7424.7 | 7577.4 | 2094.5 | 1899.9 | 0.882
%CV | 14% | 17% | 20% | 20% | -
Range | 5781 - 9552 | 5616 - 10400 | 1404 - 3184 | 1300 - 2758 | 0.70 - 1.04

The mean trough concentrations (mean Ctrough) of total IgG following IV and SC administration are presented in Table 12 for both studies.

Table 12: Mean Trough Concentrations of Total IgG (mg/mL)
 | Adult, Adolescent* |  | Child, Adolescent†
 | IV Mean Ctrough | SC Mean Ctrough | IV Mean Ctrough | SC Mean Ctrough
n | 32 | 28 | 11 | 10
Mean (mg/mL) | 9.58 | 11.4 | 9.97 | 13.25
%CV | 22.3 | 20.4 | 19 | 14
Range | 6.66-14.0 | 8.10-16.2 | 7.84-13.20 | 10.77-16.90
* Measured in plasma; † Measured in serum

In contrast to plasma total IgG levels observed with monthly IV GAMUNEX-C treatment (rapid peaks followed by a slow decline), the plasma IgG levels in subjects receiving weekly SC GAMUNEX-C therapy were relatively stable (Figure 7, adult and adolescent trial).

Figure 7: Mean Steady-state Plasma Total IgG Concentration vs. Time Curves Following IV Administration or Weekly SC Administration in Adults and Adolescents

14 CLINICAL STUDIES

PI: Intravenous Administration

In a randomized, double-blind, parallel group clinical trial with 172 subjects with primary humoral immunodeficiencies GAMUNEX-C was demonstrated to be at least as efficacious as GAMIMUNE N, 10% in the prevention of any infection, i.e., validated plus clinically defined, non-validated infections of any organ system, during a nine month treatment period.(25) Twenty-six subjects were excluded from the Per Protocol analysis (2 due to non-compliance and 24 due to protocol violations). The analysis for efficacy was based on the annual rate of bacterial infections, pneumonia, acute sinusitis and acute exacerbations of chronic sinusitis.

Table 13: Efficacy Results Per Protocol Analysis
 | No. of Subjects with at Least One Infection (%)
 | GAMUNEX®-C (n=73) | GAMIMUNE® N, 10% (n=73) | Mean Difference (90% Confidence Interval) | p-Value
Validated Infections | 9 (12%) | 17 (23%) | -0.117 (-0.220, -0.015) | 0.06
Acute Sinusitis | 4 (5%) | 10 (14%)
Exacerbation of Chronic Sinusitis | 5 (7%) | 6 (8%)
Pneumonia | 0 (0%) | 2 (3%)
Any Infection [Validated infections plus clinically defined, non-validated infections.] | 56 (77%) | 57 (78%) | -0.020 (-0.135, 0.096) | 0.78

The annual rate of validated infections (Number of Infections/year/subject) was 0.18 in the group treated with GAMUNEX-C and 0.43 in the group treated with GAMIMUNE N, 10% (p=0.023). The annual rates for any infection (validated plus clinically-defined, non-validated infections of any organ system) were 2.88 and 3.38, respectively (p=0.300).

ITP

A double-blind, randomized, parallel group clinical trial with 97 ITP subjects was carried out to test the hypothesis that GAMUNEX-C was at least as effective as GAMIMUNE N, 10% in raising platelet counts from less than or equal to 20 x10^9/L to more than 50 x10^9/L within 7 days after treatment with 2 g/kg IGIV. Twenty-four percent of the subjects were less than or equal to 16 years of age.(26)

GAMUNEX-C was demonstrated to be at least as effective as GAMIMUNE N, 10% in the treatment of adults and children with acute or chronic ITP.

Table 14: Platelet Response of Per Protocol Analysis
 | Number of Responders (percent of all subjects)
 | GAMUNEX®-C (n=39) | GAMIMUNE® N, 10% (n=42) | Mean Difference (90% Confidence Interval)
By Day 7 | 35 (90%) | 35 (83%) | 0.075 (-0.037, 0.186)
By Day 23 | 35 (90%) | 36 (86%) | 0.051 (-0.058, 0.160)
Sustained for 7 days | 29 (74%) | 25 (60%) | 0.164 (0.003, 0.330)

A trial was conducted to evaluate the clinical response to rapid infusion of GAMUNEX-C in patients with ITP. The study involved 28 chronic ITP subjects, wherein the subjects received 1 g/kg GAMUNEX-C on three occasions for treatment of relapses. The infusion rate was randomly assigned to 0.08, 0.11, or 0.14 mL/kg/min (8, 11 or 14 mg/kg/min). Pre-medication with corticosteroids to alleviate infusion-related intolerability was not permitted. Pre-treatment with antihistamines, anti-pyretics and analgesics was permitted. The average dose was approximately 1 g/kg body weight at all three prescribed rates of infusion (0.08, 0.11 and 0.14 mL/kg/min). All patients were administered each of the three planned infusions except seven subjects. Based on 21 patients per treatment group, the a posteriori power to detect twice as many drug-related adverse events between groups was 23%. Of the seven subjects that did not complete the study, five did not require additional treatment, one withdrew because he refused to participate without concomitant medication (prednisone) and one experienced an adverse event (hives); however, this was at the lowest dose rate level (0.08 mL/kg/min).

CIDP

A multi-center, randomized, double-blind, Placebo-controlled trial (The Immune Globulin Intravenous (Human), 10% Caprylate/Chromatography Purified CIDP Efficacy or ICE study) was conducted with GAMUNEX-C.(27) This study included two separately randomized periods to assess whether GAMUNEX-C was more effective than Placebo for the treatment of CIDP (assessed in the Efficacy Period for up to 24 weeks) and whether long-term administration of GAMUNEX-C could maintain long-term benefit (assessed in the 24 week Randomized Withdrawal Period).

In the Efficacy Period, there was a requirement for Rescue (crossover) to the alternate study drug if the subject did not improve and maintain this improvement until the end of the 24 week treatment period. Subjects entering the Rescue phase followed the same dosing and schedule as in the Efficacy period. Any subject who was rescued (crossed over) and did not improve and maintain this improvement was withdrawn from the study.

Subjects who completed 24 weeks treatment in the Efficacy period or Rescue phase and responded to therapy were eligible for entry into a double-blind Randomized Withdrawal Period. Eligible subjects were re-randomized to GAMUNEX-C or Placebo. Any subject who relapsed was withdrawn from the study.

The Efficacy Period and the Rescue treatment started with a loading dose of 2 g/kg body weight of GAMUNEX-C or equal volume of Placebo given over 2-4 consecutive days. All other infusions (including the first infusion of the Randomized Withdrawal Period) were given as maintenance doses of 1 g/kg body weight (or equivalent volume of Placebo) every three weeks.

The Responder rates of the GAMUNEX-C and Placebo treatment groups were measured by the INCAT score. The INCAT (Inflammatory Neuropathy Cause and Treatment) scale is used to assess functional disability of both upper and lower extremities in demyelinating polyneuropathy. The INCAT scale has upper and lower extremity components (maximum of 5 points for upper (arm disability) and maximum of 5 points for lower (leg disability)) that add up to a maximum of 10-points (0 is normal and 10 is severely incapacitated).(28) At the start of the efficacy portion of the study, the INCAT scores were as follows: Upper Extremity mean was 2.2 ± 1.0, and median was 2.0 with a range of 0 to 5; Lower Extremity mean was 1.9 ± 0.9, and median was 2.0 with a range of 1 to 5; Total Overall Score mean was 4.2 ± 1.4, and median was 4.0 with a range of 2 to 9. A Responder was defined as a subject with at least 1-point improvement from baseline in the adjusted INCAT score that was maintained through 24 weeks.

More subjects with CIDP responded to GAMUNEX-C: 28 of 59 subjects (47.5%) responded to GAMUNEX-C compared with 13 of 58 subjects (22.4%) administered Placebo (25% difference; 95% CI 7%-43%; p=0.006). The study included both subjects who were IGIV naïve and subjects who had previous IGIV experience. The outcome was influenced by the group of subjects who experienced prior therapy with IGIV, as shown by the outcomes table, below.

Time to relapse for the subset of 57 subjects who previously responded to GAMUNEX-C was evaluated: 31 were randomly reassigned to continue to receive GAMUNEX-C and 26 subjects were randomly reassigned to Placebo in the Randomized Withdrawal Period. Subjects who continued to receive GAMUNEX-C experienced a longer time to relapse versus subjects treated with Placebo (p=0.011). The probability of relapse was 13% with GAMUNEX-C versus 45% with Placebo (hazard ratio, 0.19; 95% confidence interval, 0.05, 0.70).

Table 15: Outcomes in Intent-to-Treat Population Efficacy Period
Efficacy Period | GAMUNEX®-C |  | Placebo |  | p-value [p-value based on Fisher's exact method]
Efficacy Period | Responder | Non-Responder | Responder | Non-Responder | p-value [p-value based on Fisher's exact method]
All Subjects | 28/59 (47.5%) | 31/59 (52.5%) | 13/58 (22.4%) | 45/58 (77.6%) | 0.006
IGIV - Naïve Subjects | 17/39 (43.6%) | 22/39 (56.4%) | 13/46 (28.3%) | 33/46 (71.7%) | 0.174
IGIV - Experienced Subjects | 11/20 (55.0%) | 9/20 (45.0%) | 0/12 (0%) | 12/12 (100%) | 0.002

The following table shows outcomes for the Rescue Phase (which are supportive data):

Table 16: Outcomes in Rescue Phase
Rescue Phase | GAMUNEX®-C |  | Placebo |  | p-value [p-value based on Fisher's exact method]
Rescue Phase | Success | Failure | Success | Failure | p-value [p-value based on Fisher's exact method]
All Subjects | 25/45 (55.6%) | 20/45 (44.4%) | 6/23 (26.1%) | 17/23 (73.9%) | 0.038
IGIV - Naïve Subjects | 19/33 (57.6%) | 14/33 (42.4%) | 6/18 (33.3%) | 12/18 (66.7%) | 0.144
IGIV - Experienced Subjects | 6/12 (50%) | 6/12 (50%) | 0/5 (0%) | 5/5 (100%) | 0.102

The following Kaplan-Meier curves show the outcomes for the Randomized Withdrawal Period:

Figure 8: Outcome for Randomized Withdrawal Period

Secondary Endpoint
Randomized Withdrawal Period

Time to Relapse

p-value [p-value based on log-rank test]
p= 0.011

15 REFERENCES

1. Buckley RH, Schiff RI. The use of intravenous immune globulin in immunodeficiency diseases. N Engl J Med 1991;325(2):110-7.
2. Cunningham-Rundles C, Bodian C. Common variable immunodeficiency: clinical and immunological features of 248 patients. Clin Immunol 1999;92(1):34-48.
3. Pruzanski W, Sussman G, Dorian W, et al. Relationship of the dose of intravenous gammaglobulin to the prevention of infections in adults with common variable immunodeficiency. Inflammation 1996;20(4):353-9.
4. Stephan JL, Vlekova V, Le Deist F, et al. Severe combined immunodeficiency: a retrospective single-center study of clinical presentation and outcome in 117 patients. J Pediatr 1993;123(4):564-72.
5. Blanchette VS, Kirby MA, Turner C. Role of intravenous immunoglobulin G in autoimmune hematologic disorders. Semin Hematol 1992;29(3 Suppl 2):72-82.
6. Lazarus AH, Freedman J, Semple JW. Intravenous immunoglobulin and anti-D in idiopathic thrombocytopenic purpura (ITP): mechanisms of action. Transfus Sci 1998;19(3):289-94.
7. Cayco AV, Perazella MA, Hayslett JP. Renal insufficiency after intravenous immune globulin therapy: a report of two cases and an analysis of the literature. J Am Soc Nephrol 1997;8(11):1788-94.
8. Pierce LR, Jain N. Risks associated with the use of intravenous immunoglobulin. Trans Med Rev 2003;17:241-51.
9. Steinberger BA, Ford SM, Coleman TA. Intravenous immunoglobulin therapy results in post-infusional hyperproteinemia, increased serum viscosity, and pseudohyponatremia. Am J Hematol 2003;73:97-100.
10. Dalakas MC. High-dose intravenous immunoglobulin and serum viscosity: risk of precipitating thromboembolic events. Neurology 1994;44:223-6.
11. Woodruff RK, Grigg AP, Firkin FC, et al. Fatal thrombotic events during treatment of autoimmune thrombocytopenia with intravenous immunoglobulin in elderly patients. Lancet 1986;2:217-8.
12. Wolberg AS, Kon RH, Monroe DM, et al. Coagulation factor XI is a contaminant in intravenous immunoglobulin preparations. Am J Hematol 2000;65:30-4.
13. Copelan EA, Strohm PL, Kennedy MS, et al. Hemolysis following intravenous immune globulin therapy. Transfusion 1986;26:410-2.
14. Thomas MJ, Misbah SA, Chapel HM, et al. Hemolysis after high-dose intravenous Ig. Blood 1993;15:3789.
15. Wilson JR, Bhoopalam N, Fisher M. Hemolytic anemia associated with intravenous immunoglobulin. Muscle & Nerve 1997;20:1142-5.
16. Kessary-Shoham H, Levy Y, Shoenfeld Y, et al. In vivo administration of intravenous immunoglobulin (IVIg) can lead to enhanced erythrocyte sequestration. J Autoimmune 1999;13:129-35.
17. Kahwaji J, Barker E, Pepkowitz S, et al. Acute hemolysis after high-dose intravenous immunoglobulin therapy in highly HLA sensitized patients. Clin J Am Soc Nephrol 2009;4:1993-7.
18. Daw Z, Padmore R, Neurath D, et al. Hemolytic transfusion reactions after administration of intravenous immune (gamma) globulin: A case series analysis. Transfusion 2008;48:1598-601.
19. Rizk A, Gorson KC, Kenney L, et al. Transfusion-related acute lung injury after the infusion of IVIG. Transfusion 2001;41:264-8.
20. Orbach H, Katz U, Sherer Y, et al. Intravenous immunoglobulin: adverse effects and safe administration. Clin Rev Allergy Immunol 2005;29:173-84.
21. Tai VM, Mitchell EJ, Lee-Brotherton V, et al. Safety evaluation of intravenous glycine in formulation development. J Pharm Pharmaceut Sci 2000;3:198.
22. Traul KA, Driedger A, Ingle D, et al. Review of the toxicologic properties of medium-chain triglycerides. Food Chem Toxicol 2000;38(1):79-98.
23. Barnette D, Roth NJ, Hotta J, et al. Pathogen safety profile of a 10% IgG preparation manufactured using a depth filtration-modified process. Biologicals 2012;40:247-53.
24. Wasserman RL, Irani A-M, Tracy J, et al. Pharmacokinetics and safety of subcutaneous immune globulin (human), 10% caprylate/chromatography purified in patients with primary immunodeficiency disease. Clinical and Experimental Immunology 2011;161:518-26.
25. Roifman CM, Schroeder H, Berger M, et al. Comparison of the efficacy of IGIV-C, 10% (caprylate/chromatography) and IGIV-SD, 10% as replacement therapy in primary immune deficiency. A randomized double-blind trial. Internat Immunopharmacol 2003;3:1325–33.
26. Bussell JB, Eldor A, Kelton JG, et al. IGIV-C, a novel intravenous immunoglobulin: evaluation of safety, efficacy, mechanisms of action and impact on quality of life. Thromb Haemost 2004;91:771–8.
27. Hughes RAC, Donofrio P, Bril V, et al. Intravenous immune globulin (10% caprylate/chromatography purified) for the treatment of chronic inflammatory demyelinating polyradiculoneuropathy (ICE study): a randomised placebo-controlled trial. Lancet Neurol 2008;7:136-44.
28. Hughes R, Bensa S, Willison H, et al. Randomized controlled trial of intravenous immunoglobulin versus oral prednisolone in chronic inflammatory demyelinating polyradiculoneuropathy. Ann Neurol 2001;50(2):195-201.

16 HOW SUPPLIED/STORAGE AND HANDLING

GAMUNEX-C is supplied in single-use, tamper evident vials (shrink band) containing the labeled amount of functionally active IgG. The four larger vial size labels incorporate integrated hangers. GAMUNEX-C is not made with natural rubber latex.

GAMUNEX-C is supplied in the following sizes:

NDC Number | Size | Grams Protein
13533-800-12 | 10 mL | 1
13533-800-15 | 25 mL | 2.5
13533-800-20 | 50 mL | 5
13533-800-71 | 100 mL | 10
13533-800-24 | 200 mL | 20
13533-800-40 | 400 mL | 40

- DO NOT FREEZE
- Keep the vial in the carton to protect from light.
- GAMUNEX-C may be stored for 36 months at 2-8°C (36-46°F) from the date of manufacture, AND product may be stored at temperatures not to exceed 25°C (77°F) for up to 6 months anytime during the 36 month shelf life, after which the product must be immediately used or discarded.
- Do not use after expiration date.

17 PATIENT COUNSELING INFORMATION

[see Boxed Warning and Warnings and Precautions]

Instruct patients to immediately report the following signs and symptoms to their healthcare provider:

- Decreased urine output, sudden weight gain, fluid retention/edema, and/or shortness of breath [see Warnings and Precautions (5.2)]
- Symptoms of thrombosis which may include: pain and/or swelling of an arm or leg with warmth over the affected area, discoloration of an arm or leg, unexplained shortness of breath, chest pain or discomfort that worsens on deep breathing, unexplained rapid pulse, numbness or weakness on one side of the body [see Warnings and Precautions (5.4)]
- Severe headache, neck stiffness, drowsiness, fever, sensitivity to light, painful eye movements, nausea, and vomiting [see Warnings and Precautions (5.5)]
- Increased heart rate, fatigue, yellowing of the skin or eyes, and dark-colored urine [see Warnings and Precautions (5.6)]
- Trouble breathing, chest pain, blue lips or extremities, and fever [see Warnings and Precautions (5.7)]

Inform patients that GAMUNEX-C is made from human plasma and may contain infectious agents that can cause disease. While the risk GAMUNEX-C can transmit an infectious agent has been reduced by screening plasma donors for prior exposure, testing donated plasma, and by inactivating or removing pathogens during manufacturing, patients should report any symptoms that concern them. [see Warnings and Precautions (5.9)]

Inform patients that GAMUNEX-C can interfere with their immune response to live virus vaccines such as measles, mumps and rubella. Inform patients to notify their healthcare professional of this potential interaction when they are receiving vaccinations. [see Drug Interactions (7)]

PI: Self-Administration: Subcutaneous Administration Only

Advise the patient to read the FDA-approved patient labeling (Instructions for Use: Subcutaneous Infusion for Primary Humoral Immunodeficiency).

Provide the patient with instructions on subcutaneous infusion for home treatment, if the physician believes that home administration is appropriate for the patient.

- The type of equipment to be used along with its maintenance,
- proper infusion techniques, selection of appropriate infusion sites (e.g., abdomen, thighs, upper arms, and/or lateral hip),
- maintenance of a treatment diary, and
- measures to be taken in case of adverse reactions in the patient instructions.

Manufactured by:
Grifols Therapeutics LLC
Research Triangle Park, NC 27709 USA
U.S. License No. 1871
3054846/3054847/3056967/3058072

GAMUNEX®-C

Immune Globulin Injection (Human),
10% Caprylate/Chromatography Purified

Instructions for Use: Subcutaneous Infusion for
Primary Humoral Immunodeficiency

Information for Patients
Please read this information about GAMUNEX-C carefully before using this medicine. This information does not take the place of talking with your healthcare professional, and it does not include all of the important information about GAMUNEX-C. If you have any questions after reading this, contact your healthcare professional.

What is the most important information I should know about GAMUNEX-C?
GAMUNEX-C should be infused under your skin (in the subcutaneous tissue). DO NOT inject GAMUNEX-C into a blood vessel or directly into a muscle.

What is GAMUNEX-C?
GAMUNEX-C (Găm-yōō-nĕx) is an immunoglobulin used to treat primary immune deficiency (PI). Immunoglobulin is another name for the purified antibodies from human plasma that defend the body against infections such as viruses and bacteria. People with PI lack the healthy antibodies needed to fight off these infections. GAMUNEX-C provides those healthy antibodies and will help lower the number and severity of infections you could get.

Who should NOT take GAMUNEX-C?
Do not take GAMUNEX-C if you have known severe allergic reactions or a severe response to Immune Globulin (Human). Tell your doctor if you have had a serious reaction to other medicines that contain immune globulin. Also tell your doctor if you have an immunoglobulin A (IgA) deficiency.

How should I take GAMUNEX-C?
You will take GAMUNEX-C through infusions given just below the skin (in the subcutaneous tissue). As directed by your physician, one or more injection sites on your body will be selected. The number and location of the injection sites depends on the amount you need to receive. Typically, adults may use 1 to 4 needles in different locations at one time. You may use up to 8 needles as directed by your doctor. For children, use up to 6 infusion sites simultaneously. For patients of all ages ensure that the infusion sites are at least 2 inches (5 cm) apart. The needles are attached with a tube to the pump. You will need to have infusions once a week.

Instructions for administering GAMUNEX-C are at the end of this patient Instructions for Use [see "Steps for Administration"]. Only use GAMUNEX-C by yourself after you have been instructed by your doctor or healthcare professional.

What should I avoid while taking GAMUNEX-C?
Certain types of vaccines (ones containing a live virus) may not work as well for you if you are also receiving immunoglobulin products like GAMUNEX-C. The antibodies in GAMUNEX-C may prevent the vaccine from working. Before you get a vaccine, tell the doctor or nurse that you are taking GAMUNEX-C.

Tell your doctor or healthcare professional if you are pregnant or plan to become pregnant, or if you are nursing.

What are possible side effects of GAMUNEX-C?
The most common side effects with GAMUNEX-C when given under the skin (subcutaneously) are:

- Redness, swelling, and itching at the injection site
- Fatigue
- Headache
- Pain (including pain in the joints, arms, legs)
- Diarrhea
- Nausea
- Migraine
- Fever

Tell your doctor right away or go to the emergency room if you have hives, trouble breathing, wheezing, dizziness, or fainting. These could be signs of a bad allergic reaction.

Tell your doctor right away if you have any of the following symptoms. They could be signs of a rare, but serious problem.

- Decreased urination, sudden weight gain, fluid retention/swelling in your legs, and/or shortness of breath. They could be signs of a serious kidney problem called renal failure.
- Pain and/or swelling of an arm or leg with warmth over the affected area, discoloration of an arm or leg, unexplained shortness of breath, chest pain or discomfort that worsens on deep breathing, unexplained rapid pulse, numbness or weakness on one side of the body. These could be signs of a blood clot in your body (thrombosis). Immediately report symptoms of thrombosis.
- Severe headache, stiff neck, fatigue, fever, sensitivity to light, painful eye movements, nausea and vomiting. These could be signs of a type of brain inflammation called aseptic meningitis.
- Increased heart rate, fatigue, yellow skin or eyes, and dark colored urine. These could be signs of a type of blood problem called hemolytic anemia.
- Chest pains, trouble breathing, blue lips or extremities, and fever. These could be signs of a lung problem called TRALI (transfusion-related acute lung injury).
- Fever over 100°F (37.8oC). This could be a sign of an infection.

Tell your doctor about any side effects that concern you. You can ask your doctor to give you the full prescribing information available to healthcare professionals.

Steps for Administration
Infuse GAMUNEX-C only after you have been trained by your doctor or healthcare professional. Below are step-by-step instructions to help you remember how to use GAMUNEX-C. Ask your doctor or healthcare professional about any instructions you do not understand.

Before Using GAMUNEX-C

- GAMUNEX-C comes in single-use vials.
- Keep it refrigerated. Do not let it freeze.
- Keep the vial in the carton to protect from light.
- GAMUNEX-C can be stored at room temperature for up to 6 months but you must use it within that time or you must throw it away.
- Do not shake the vials.
- Prior to use, allow the solution to come to room temperature (68-77°F or 20-25°C). This can take 60 minutes or longer.
- Do not use the vial if:
  - the solution is cloudy, discolored or contains particles. The solution should be clear to opalescent, and colorless to pale yellow.
  - the protective cap or plastic shrink band around the cap is missing, or there is any evidence of tampering. Tell your healthcare provider immediately.
  - the expiration date has passed.
- Sanitize your infusion set-up area by preparing a clean, flat, non-porous surface such as a kitchen counter. Avoid using porous surfaces such as wood. Clean the surface with an alcohol wipe using a circular motion from the center outward.

Step 1:
Wash and dry your hands thoroughly before administering GAMUNEX-C

- Your healthcare provider may recommend that you use antibacterial soap or that you wear gloves.

Step 2:
Remove the protective cap and sanitize the stopper

- Remove the protective cap from the vial to expose the central portion of the stopper.
- Wipe the stopper with alcohol and allow to dry.

Step 3:
Use aseptic technique when preparing and administering GAMUNEX-C

- Do not allow your fingers or other objects to touch the inner stem of the plunger, the syringe tip, or other areas that will come in contact with your GAMUNEX-C solution. This is called aseptic technique and is designed to prevent transmission of germs.
- Using aseptic technique, attach each needle to the syringe tip.

Step 4:
Prepare the syringe and draw GAMUNEX-C solution into syringe

- Remove cap from needle.
- Pull the syringe plunger back to the level matching the amount of GAMUNEX-C to be withdrawn from the vial.
- Place the GAMUNEX-C vial on a clean flat surface and insert the needle into the center of the vial stopper.
- Inject air into the vial. The amount of air should match the amount of GAMUNEX-C to be withdrawn.
- Turn the vial upside down and withdraw the correct amount of GAMUNEX-C. If multiple vials are required to achieve the correct dose, repeat Step 4.

Step 5:
Fill the pump reservoir and prepare the infusion pump

- Follow the pump manufacturer’s instructions for filling the pump reservoir and preparing the infusion pump, administration tubing and Y-site connection tubing, if needed.
- Be sure to prime the administration tubing to ensure that no air is left in the tubing or needle by filling the tubing/needle with GAMUNEX-C. To prime, hold the syringe in one hand and the administration tubing’s capped needle in the other. Gently squeeze on the plunger until you see a drop of GAMUNEX-C exit from the needle.

Example Equipment

Step 6:
Select the number and location of infusion sites

- Select one or more infusion sites as directed by your healthcare provider.
- The number and location of injection sites depends on the volume of the total dose.

Step 7:
Prepare the infusion site

- Cleanse the infusion site(s) with antiseptic solution using a circular motion working from the center of the site and moving to the outside.
- Sites should be clean, dry, and at least 2 inches apart.

Step 8:
Insert the needle

- Grasp the skin between two fingers and insert the needle into the subcutaneous tissue.

Step 9:
Do not inject GAMUNEX-C into a blood vessel

- After inserting each needle into tissue (and before your infusion), make sure that a blood vessel has not been accidentally entered. To do this, attach a sterile syringe to the end of the primed administration tubing. Pull back on the syringe plunger and watch for any blood flowing back into administration tubing.
- If you see any blood, remove and discard the needle and administration tubing.

- Repeat priming and needle insertion steps using a new needle, administration tubing and a new infusion site.
- Secure the needle in place by applying sterile gauze or transparent dressing over the site.

Step 10:
Repeat for other sites, as needed

- If using multiple, simultaneous infusion sites, use Y-site connection tubing and secure to the administration tubing.

Step 11:
Infuse GAMUNEX-C following the pump manufacturer’s instructions for the infusion pump

Step 12:
After infusion, turn off pump and dispose of used supplies

- Follow manufacturer’s instructions to turn off pump.
- Undo and discard any dressing or tape.
- Gently remove the inserted needle(s) or catheter(s).
- Discard any unused solution in an appropriate waste container as instructed.
- Discard any used administration equipment in an appropriate waste container.
- Store your supplies in a safe place.
- Follow manufacturer’s instructions to care for the infusion pump.

Step 13:
Record each infusion

- Remove the peel-off label with the product lot number from the GAMUNEX-C vial and use this to complete the patient record.
- Remember to bring your journal with you when you visit your physician or healthcare provider.

Be sure to tell your doctor about any problems you have doing your infusions. Your doctor may ask to see your journal, so be sure to take it with you each time you visit the doctor’s office.

Call your doctor for medical advice about side effects. You can also report side effects to FDA at 1-800-FDA-1088 or www.fda.gov/medwatch.

Manufactured by:
Grifols Therapeutics LLC
Research Triangle Park, NC 27709 USA
U.S. License No. 1871

Revised 1/2020
3054846/3054847/3056967/3058072

PACKAGE LABEL

NDC 13533-800-71 10 g / 100 mL
Immune Globulin
Injection (Human), 10%
gamunex®-c
Caprylate/Chromatography Purified
Solution for Infusion
Rx only
For intravenous or
subcutaneous administration
GRIFOLS
Contents:
One vial of Gamunex-C
No preservative
Sterile, Non-pyrogenic
Keep the vial in the carton to protect from
light.
Gamunex-C may be stored for 36 months
at 2–8°C (36–46°F), AND product may be
stored at temperatures not to exceed 25°C
(77°F) for up to 6 months anytime during the
36 month shelf life, after which the product
must be immediately used or discarded.
Date removed
from refrigeration:
GRIFOLS
NDC 13533-800-71 10 g / 100 mL
Immune Globulin
Injection (Human), 10%
gamunex®-c
Caprylate/Chromatography Purified
Solution for Infusion
Rx only
For intravenous or
subcutaneous administration
GRIFOLS
The patient and physician should discuss the
risks and benefits of this product.
Refer to package insert for dosage and
administration and compatibility with
other solutions.
Single-dose Vial
Do not use if turbid.
Discard unused portion. Do not store after
entry into vial.
Contains no preservative.
Do not freeze.
Each milliliter (mL) contains approximately
100 mg of protein, not less than 98% of which
is immunoglobulin, and approximately 15 mg
glycine.
If the shrink band is absent or shows any
sign of tampering, do not use the product and
notify Grifols Therapeutics LLC immediately.
Not Returnable for Credit or Exchange.
Grifols Therapeutics LLC
Research Triangle Park, NC 27709 USA
U.S. License No. 1871
GRIFOLS
Carton: 3060376
GTIN 00313533800710
LOT XXXXXXXXXX
EXP DDMMMYYYY
SN XXXXXXXXXXXXXXXX
NDC 13533-800-71 10 g / 100 mL
Immune Globulin
Injection (Human), 10%
gamunex®-c

NDC 13533-800-72 10 g / 100 mL
Immune Globulin
Injection (Human), 10%
gamunex®-c
Caprylate/Chromatography Purified
Solution for Infusion
Rx only
For intravenous or subcutaneous administration
The patient and physician should discuss the risks and
benefits of this product.
Refer to package insert for dosage and administration and
compatibility with other solutions.
Gamunex-C may be stored for 36 months at 2–8°C
(36–46°F), AND product may be stored at temperatures
not to exceed 25°C (77°F) for up to 6 months anytime
during the 36 month shelf life, after which the product
must be immediately used or discarded.
Single-dose Vial
Do not use if turbid.
Grifols Therapeutics LLC
Research Triangle Park, NC 27709 USA
U.S. License No. 1871
Gamunex-C 10 g / 100 mL
Lot
3062521
Lot
Exp